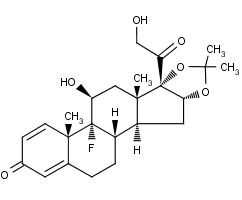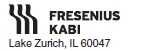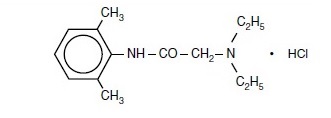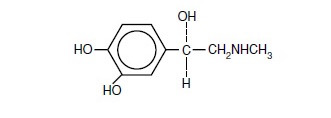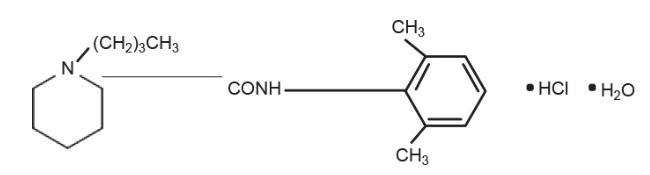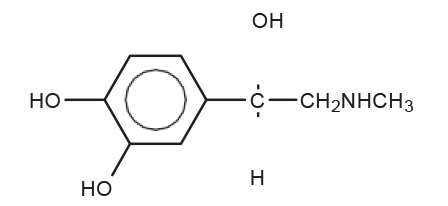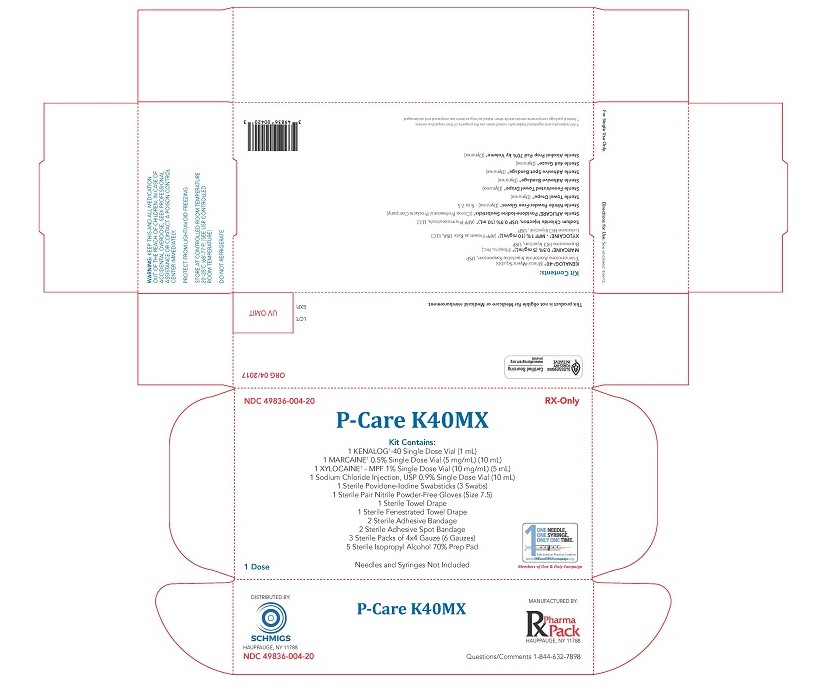 DRUG LABEL: P-Care K40MX
NDC: 49836-004 | Form: KIT | Route: TOPICAL
Manufacturer: RX PHARMA-PACK, INC.
Category: prescription | Type: HUMAN PRESCRIPTION DRUG LABEL
Date: 20200203

ACTIVE INGREDIENTS: POVIDONE-IODINE 10 mg/1 mL; ISOPROPYL ALCOHOL 0.7 mL/1 mL; LIDOCAINE HYDROCHLORIDE ANHYDROUS 10 mg/1 mL; SODIUM CHLORIDE 9 mg/1 mL; BUPIVACAINE HYDROCHLORIDE 5 mg/1 mL; TRIAMCINOLONE ACETONIDE 40 mg/1 mL
INACTIVE INGREDIENTS: SODIUM PHOSPHATE, DIBASIC; CITRIC ACID MONOHYDRATE; SODIUM HYDROXIDE; NONOXYNOL-9; WATER; WATER; SODIUM CHLORIDE 7 mg/1 mL; SODIUM HYDROXIDE; HYDROCHLORIC ACID; HYDROCHLORIC ACID; SODIUM HYDROXIDE; SODIUM CHLORIDE; SODIUM HYDROXIDE; HYDROCHLORIC ACID; WATER; SODIUM CHLORIDE; BENZYL ALCOHOL; POLYSORBATE 80; SODIUM HYDROXIDE; HYDROCHLORIC ACID; NITROGEN; CARBOXYMETHYLCELLULOSE SODIUM

P-Care K40MX

KENALOG-40 Injection - triamcinolone acetonide injection, suspension

KENALOG®-40 INJECTION
(triamcinolone acetonide injectable suspension, USP)

E.R. Squibb & Sons, L.L.C.

NOT FOR USE IN NEONATES CONTAINS BENZYL ALCOHOL

For Intramuscular or Intra-articular Use Only

NOT FOR INTRAVENOUS, INTRADERMAL, INTRAOCULAR, EPIDURAL, OR INTRATHECAL USE

DESCRIPTION

Kenalog®-40 Injection and Kenalog®-80 Injection (triamcinolone acetonide injectable suspension, USP) are a synthetic glucocorticoid corticosteroid with anti-inflammatory action. THESE FORMULATIONS ARE SUITABLE FOR INTRAMUSCULAR AND INTRA-ARTICULAR USE ONLY. THESE FORMULATIONS ARE NOT FOR INTRADERMAL INJECTION.

Kenalog®-40 Injection: Each mL of the sterile aqueous suspension provides 40 mg triamcinolone acetonide, with 0.66% sodium chloride for isotonicity, 0.99% (w/v) benzyl alcohol as a preservative, 0.63% carboxymethylcellulose sodium, and 0.04% polysorbate 80. Sodium hydroxide or hydrochloric acid may be present to adjust pH to 5.0 to 7.5. At the time of manufacture, the air in the container is replaced by nitrogen.

Kenalog®-80 Injection: Each mL of the sterile aqueous suspension provides 80 mg triamcinolone acetonide, with 0.66% sodium chloride for isotonicity, 0.99% (w/v) benzyl alcohol as a preservative, 0.63% carboxymethylcellulose sodium, and 0.04% polysorbate 80. Sodium hydroxide or hydrochloric acid may be present to adjust pH to 5.0 to 7.5. At the time of manufacture, the air in the container is replaced by nitrogen.

The chemical name for triamcinolone acetonide is 9-Fluoro-11β,16α,17,21-tetrahydroxypregna-1,4-diene-3,20-dione cyclic 16,17-acetal with acetone. Its structural formula is:

Kenalog-40 Structural Formula

Triamcinolone acetonide occurs as a white to cream-colored, crystalline powder having not more than a slight odor and is practically insoluble in water and very soluble in alcohol.

CLINICAL PHARMACOLOGY

Glucocorticoids, naturally occurring and synthetic, are adrenocortical steroids that are readily absorbed from the gastrointestinal tract.

Naturally occurring glucocorticoids (hydrocortisone and cortisone), which also have salt-retaining properties, are used as replacement therapy in adrenocortical deficiency states. Synthetic analogs such as triamcinolone are primarily used for their anti-inflammatory effects in disorders of many organ systems.

Kenalog-40 Injection and Kenalog-80 Injection have an extended duration of effect which may be sustained over a period of several weeks. Studies indicate that following a single intramuscular dose of 60 mg to 100 mg of triamcinolone acetonide, adrenal suppression occurs within 24 to 48 hours and then gradually returns to normal, usually in 30 to 40 days. This finding correlates closely with the extended duration of therapeutic action achieved with the drug.

INDICATIONS AND USAGE

Intramuscular
Where oral therapy is not feasible, injectable corticosteroid therapy, including Kenalog-40 Injection and Kenalog-80 Injection (triamcinolone acetonide injectable suspension, USP) are indicated for intramuscular use as follows:
Allergic states: Control of severe or incapacitating allergic conditions intractable to adequate trials of conventional treatment in asthma, atopic dermatitis, contact dermatitis, drug hypersensitivity reactions, perennial or seasonal allergic rhinitis, serum sickness, transfusion reactions.

Dermatologic diseases: Bullous dermatitis herpetiformis, exfoliative erythroderma, mycosis fungoides, pemphigus, severe erythema multiforme (Stevens-Johnson syndrome).

Endocrine disorders: Primary or secondary adrenocortical insufficiency (hydrocortisone or cortisone is the drug of choice; synthetic analogs may be used in conjunction with mineralocorticoids where applicable; in infancy, mineralocorticoid supplementation is of particular importance), congenital adrenal hyperplasia, hypercalcemia associated with cancer, nonsuppurative thyroiditis.

Gastrointestinal diseases: To tide the patient over a critical period of the disease in regional enteritis and ulcerative colitis.

Hematologic disorders: Acquired (autoimmune) hemolytic anemia, Diamond-Blackfan anemia, pure red cell aplasia, selected cases of secondary thrombocytopenia.

Miscellaneous: Trichinosis with neurologic or myocardial involvement, tuberculous meningitis with subarachnoid block or impending block when used with appropriate antituberculous chemotherapy.

Neoplastic diseases: For the palliative management of leukemias and lymphomas.

Nervous system: Acute exacerbations of multiple sclerosis; cerebral edema associated with primary or metastatic brain tumor or craniotomy.

Ophthalmic diseases: Sympathetic ophthalmia, temporal arteritis, uveitis, and ocular inflammatory conditions unresponsive to topical corticosteroids.

Renal diseases: To induce diuresis or remission of proteinuria in idiopathic nephrotic syndrome or that due to lupus erythematosus.

Respiratory diseases: Berylliosis, fulminating or disseminated pulmonary tuberculosis when used concurrently with appropriate antituberculous chemotherapy, idiopathic eosinophilic pneumonias, symptomatic sarcoidosis.

Rheumatic disorders: As adjunctive therapy for short-term administration (to tide the patient over an acute episode or exacerbation) in acute gouty arthritis; acute rheumatic carditis; ankylosing spondylitis; psoriatic arthritis; rheumatoid arthritis, including juvenile rheumatoid arthritis (selected cases may require low-dose maintenance therapy). For the treatment of dermatomyositis, polymyositis, and systemic lupus erythematosus.

Intra-Articular
The intra-articular or soft tis sue administration of Kenalog-40 Injection and Kenalog-80 Injection are indicated as adjunctive therapy for short-term administration (to tide the patient over an acute episode or exacerbation) in acute gouty arthritis, acute and subacute bursitis, acute nonspecific tenosynovitis, epicondylitis, rheumatoid arthritis, synovitis of osteoarthritis.

CONTRAINDICATIONS

Kenalog-40 Injection and Kenalog-80 Injection are contraindicated in patients who are hypersensitive to any components of this product (see WARNINGS: General).

Intramuscular corticosteroid preparations are contraindicated for idiopathic thrombocytopenic purpura.

WARNINGS

Serious Neurologic Adverse Reactions with Epidural Administration
Serious neurologic events, some resulting in death, have been reported with epidural injection of corticosteroids (see WARNINGS: Neurologic). Specific events reported include, but are not limited to, spinal cord infarction, paraplegia, quadriplegia, cortical blindness, and stroke. These serious neurologic events have been reported with and without use of fluoroscopy. The safety and effectiveness of epidural administration of corticosteroids have not been established, and corticosteroids are not approved for this use.

General
Exposure to excessive amounts of benzyl alcohol has been associated with toxicity (hypotension, metabolic acidosis), particularly in neonates, and an increased incidence of kernicterus, particularly in small preterm infants. There have been rare reports of deaths, primarily in preterm infants, associated with exposure to excessive amounts of benzyl alcohol. The amount of benzyl alcohol from medications is usually considered negligible compared to that received in flush solutions containing benzyl alcohol. Administration of high dosages of medications containing this preservative must take into account the total amount of benzyl alcohol administered. The amount of benzyl alcohol at which toxicity may occur is not known. If the patient requires more than the recommended dosages or other medications containing this preservative, the practitioner must consider the daily metabolic load of benzyl alcohol from these combined sources (see PRECAUTIONS: Pediatric Use).

Rare instances of anaphylaxis have occurred in patients receiving corticosteroid therapy (see ADVERSE REACTIONS). Cases of serious anaphylaxis, including death, have been reported in individuals receiving triamcinolone acetonide injection, regardless of the route of administration.

Because Kenalog-40 Injection and Kenalog-80 Injection (triamcinolone acetonide injectable suspension, USP) are suspensions, they should not be administered intravenously.

Unless a deep intramuscular injection is given, local atrophy is likely to occur. (For recommendations on injection techniques, see DOSAGE AND ADMINISTRATION.) Due to the significantly higher incidence of local atrophy when the material is injected into the deltoid area, this injection site should
be avoided in favor of the gluteal area.

Increased dosage of rapidly acting corticosteroids is indicated in patients on corticosteroid therapy subjected to any unusual stress before, during, and after the stressful situation. Kenalog-40 Injection and Kenalog-80 Injection are long-acting preparations, and are not suitable for use in acute stress situations.
To avoid drug-induced adrenal insufficiency, supportive dosage may be required in times of stress (such as trauma, surgery, or severe illness) both during treatment with Kenalog-40 Injection or Kenalog-80 Injection and for a year afterwards.

Results from one multicenter, randomized, placebo-controlled study with methylprednisolone hemisuccinate, an intravenous corticosteroid, showed an increase in early (at 2 weeks) and late (at 6 months) mortality in patients with cranial trauma who were determined not to have other clear indications for corticosteroid treatment. High doses of systemic corticosteroids, including Kenalog-40 Injection and Kenalog-80 Injection, should not be used for the treatment of traumatic brain injury.

Cardio-Renal
Average and large doses of corticosteroids can cause elevation of blood pressure, salt and water retention, and increased excretion of potassium. These effects are less likely to occur with the synthetic derivatives except when they are used in large doses. Dietary salt restriction and potassium supplementation may be necessary (see PRECAUTIONS). All corticosteroids increase calcium excretion.

Literature reports suggest an apparent association between use of corticosteroids and left ventricular free wall rupture after a recent myocardial infarction; therefore, therapy with corticosteroids should be used with great caution in these patients.

Endocrine
Corticosteroids can produce reversible hypothalamic-pituitary-adrenal (HPA) axis suppression with the potential for glucocorticosteroid insufficiency after withdrawal of treatment. Metabolic clearance of corticosteroids is decreased in hypothyroid patients and increased in hyperthyroid patients. Changes in thyroid status of the patient may necessitate adjustment in dosage.

Infections

General
Patients who are on corticosteroids are more susceptible to infections than are healthy individuals. There may be decreased resistance and inability to localize infection when corticosteroids are used. Infection with any pathogen (viral, bacterial, fungal, protozoan, or helminthic) in any location of the body may be associated with the use of corticosteroids alone or in combination with other immunosuppressive agents. These infections may be mild to severe. With
increasing doses of corticosteroids, the rate of occurrence of infectious complications increases. Corticosteroids may also mask some signs of current infection.

Fungal Infections
Corticosteroids may exacerbate systemic fungal infections and therefore should not be used in the presence of such infections unless they are needed to control drug reactions. There have been cases reported in which concomitant use of amphotericin B and hydrocortisone was followed by cardiac enlargement and congestive heart failure (see PRECAUTIONS: Drug Interactions : Amphotericin B injection and potassium-depleting agents).

Special Pathogens
Latent disease may be activated or there may be an exacerbation of intercurrent infections due to pathogens, including those caused by Amoeba, Candida, Cryptococcus, Mycobacterium, Nocardia, Pneumocystis, or Toxoplasma.

It is recommended that latent amebiasis or active amebiasis be ruled out before initiating corticosteroid therapy in any patient who has spent time in the tropics or in any patient with unexplained diarrhea.

Similarly, corticosteroids should be used with great care in patients with known or suspected Strongyloides (threadworm) infestation. In such patients, corticosteroid-induced immunosuppression may lead to Strongyloides hyperinfection and dissemination with widespread larval migration, often accompanied by severe enterocolitis and potentially fatal gram-negative septicemia. Corticosteroids should not be used in cerebral malaria.

Tuberculosis
The use of corticosteroids in patients with active tuberculosis should be restricted to those cases of fulminating or disseminated tuberculosis in which the corticosteroid is used for the management of the disease in conjunction with an appropriate anti-tuberculosis regimen. If corticosteroids are indicated in patients with latent tuberculosis or tuberculin reactivity, close observation is necessary as reactivation of the disease may occur. During prolonged corticosteroid therapy, these patients should receive chemoprophylaxis.

Vaccination
Administration of live or live, attenuated vaccines is contraindicated in patients receiving immunosuppressive doses of corticosteroids. Killed or inactivated vaccines may be administered. However, the response to such vaccines cannot be predicted. Immunization procedures may be undertaken in patients who are receiving corticosteroids as replacement therapy, e.g., for Addison’s disease.

Viral Infections
Chicken pox and measles can have a more serious or even fatal course in pediatric and adult patients on corticosteroids. In pediatric and adult patients who have not had these diseases, particular care should be taken to avoid exposure. The contribution of the underlying disease and/or prior corticosteroid treatment to the risk is also not known. If exposed to chicken pox, prophylaxis with varicella zoster immune globulin (VZIG) may be indicated. If exposed to measles, prophylaxis with immunoglobulin (IG) may be indicated. (See the respective package inserts for complete VZIG and IG prescribing information.) If chicken pox develops, treatment with antiviral agents should be considered.

Neurologic
Epidural and intrathecal administration of this product is not recommended. Reports of serious medical events, including death, have been associated with epidural and intrathecal routes of corticosteroid administration (see ADVERSE REACTIONS: Gastrointestinal and Neurologic/Psychiatric).

Ophthalmic
Use of corticosteroids may produce posterior subcapsular cataracts, glaucoma with possible damage to the optic nerves, and may enhance the establishment of secondary ocular infections due to bacteria, fungi, or viruses. The use of oral corticosteroids is not recommended in the treatment of
optic neuritis and may lead to an increase in the risk of new episodes. Corticosteroids should not be used in active ocular herpes simplex.

Adequate studies to demonstrate the safety of Kenalog-40 Injection and Kenalog-80 Injection use by intraturbinal, subconjunctival, sub-Tenons, retrobulbar, and intraocular (intravitreal) injections have not been performed. Endophthalmitis, eye inflammation, increased intraocular pressure, and visual disturbances including vision loss have been reported with intravitreal administration. Administration of Kenalog-40 Injection and Kenalog-80 Injection intraocularly or into the nasal turbinates is not recommended.

Intraocular injection of corticosteroid formulations containing benzyl alcohol, such as Kenalog-40 Injection, is not recommended because of potential toxicity from the benzyl alcohol.

PRECAUTIONS

General
This product, like many other steroid formulations, is sensitive to heat. Therefore, it should not be autoclaved when it is desirable to sterilize the exterior of the vial.

The lowest possible dose of corticosteroid should be used to control the condition under treatment. When reduction in dosage is possible, the reduction should be gradual.

Since complications of treatment with glucocorticoids are dependent on the size of the dose and the duration of treatment, a risk/benefit decision must be made in each individual case as to dose and duration of treatment and as to whether daily or intermittent therapy should be used.

Kaposi’s sarcoma has been reported to occur in patients receiving corticosteroid therapy, most often for chronic conditions. Discontinuation of corticosteroids may result in clinical improvement.

Cardio-Renal
As sodium retention with resultant edema and potassium loss may occur in patients receiving corticosteroids, these agents should be used with caution in patients with congestive heart failure, hypertension, or renal insufficiency.

Endocrine
Drug-induced secondary adrenocortical insufficiency may be minimized by gradual reduction of dosage. This type of relative insufficiency may persist for months after discontinuation of therapy; therefore, in any situation of stress occurring during that period, hormone therapy should be reinstituted. Since mineralocorticoid secretion may be impaired, salt and/or a mineralocorticoid should be administered concurrently.

Gastrointestinal
Steroids should be used with caution in active or latent peptic ulcers, diverticulitis, fresh intestinal anastomoses, and nonspecific ulcerative colitis, since they may increase the risk of a perforation.

Signs of peritoneal irritation following gastrointestinal perforation in patients receiving corticosteroids may be minimal or absent.

There is an enhanced effect of corticosteroids in patients with cirrhosis.

Intra-Articular and Soft Tissue Administration
Intra-articularly injected corticosteroids may be systemically absorbed.

Appropriate examination of any joint fluid present is necessary to exclude a septic process.

A marked increase in pain accompanied by local swelling, further restriction of joint motion, fever, and malaise are suggestive of septic arthritis. If this complication occurs and the diagnosis of sepsis is confirmed, appropriate antimicrobial therapy should be instituted.

Injection of a steroid into an infected site is to be avoided. Local injection of a steroid into a previously infected joint is not usually recommended.

Corticosteroid injection into unstable joints is generally not recommended.

Intra-articular injection may result in damage to joint tissues (see ADVERSE REACTIONS: Musculoskeletal).

Musculoskeletal
Corticosteroids decrease bone formation and increase bone resorption both through their effect on calcium regulation (i.e., decreasing absorption and increasing excretion) and inhibition of osteoblast function. This, together with a decrease in the protein matrix of the bone secondary to an increase
in protein catabolism, and reduced sex hormone production, may lead to inhibition of bone growth in pediatric patients and the development of osteoporosis at any age. Special consideration should be given to patients at increased risk of osteoporosis (i.e., postmenopausal women) before initiating corticosteroid therapy.

Neuro-Psychiatric
Although controlled clinical trials have shown corticosteroids to be effective in speeding the resolution of acute exacerbations of multiple sclerosis, they do not show that they affect the ultimate outcome or natural history of the disease. The studies do show that relatively high doses of corticosteroids are necessary to demonstrate a significant effect. (See DOSAGE AND ADMINISTRATION.)

An acute myopathy has been observed with the use of high doses of corticosteroids, most often occurring in patients with disorders of neuromuscular transmission (e.g., myasthenia gravis), or in patients receiving concomitant therapy with neuromuscular blocking drugs (e.g., pancuronium). This acute myopathy is generalized, may involve ocular and respiratory muscles, and may result in quadriparesis. Elevation of creatinine kinase may occur. Clinical improvement or recovery after stopping corticosteroids may require weeks to years.

Psychiatric derangements may appear when corticosteroids are used, ranging from euphoria, insomnia, mood swings, personality changes, and severe depression to frank psychotic manifestations. Also, existing emotional instability or psychotic tendencies may be aggravated by corticosteroids.

Ophthalmic
Intraocular pressure may become elevated in some individuals. If steroid therapy is continued for more than 6 weeks, intraocular pressure should be monitored.

Information for Patients
Patients should be warned not to discontinue the use of corticosteroids abruptly or without medical supervision, to advise any medical attendants that they are taking corticosteroids, and to seek medical advice at once should they develop fever or other signs of infection.

Persons who are on corticosteroids should be warned to avoid exposure to chicken pox or measles. Patients should also be advised that if they are exposed, medical advice should be sought without delay.

Drug Interactions
Aminoglutethimide: Aminoglutethimide may lead to a loss of corticosteroid-induced adrenal suppression.

Amphotericin B injection and potassium-depleting agents: When corticosteroids are administered concomitantly with potassium-depleting agents (i.e., amphotericin B, diuretics), patients should be observed closely for development of hypokalemia. There have been cases reported in which concomitant use of amphotericin B and hydrocortisone was followed by cardiac enlargement and congestive heart failure.

Antibiotics: Macrolide antibiotics have been reported to cause a significant decrease in corticosteroid clearance.

Anticholinesterases: Concomitant use of anticholinesterase agents and corticosteroids may produce severe weakness in patients with myasthenia gravis. If possible, anticholinesterase agents should be withdrawn at least 24 hours before initiating corticosteroid therapy.

Anticoagulants, oral: Coadministration of corticosteroids and warfarin usually results in inhibition of response to warfarin, although there have been some conflicting reports. Therefore, coagulation indices should be monitored frequently to maintain the desired anticoagulant effect.

Antidiabetics: Because corticosteroids may increase blood glucose concentrations, dosage adjustments of antidiabetic agents may be required.

Antitubercular drugs: Serum concentrations of isoniazid may be decreased.

Cholestyramine: Cholestyramine may increase the clearance of corticosteroids.

Cyclosporine: Increased activity of both cyclosporine and corticosteroids ma occur when the two are used concurrently. Convulsions have been reported with this concurrent use.

CYP3A4 inhibitors: Triamcinolone acetonide is a substrate of CYP3A4. Ketoconazole has been reported to decrease the metabolism of certain corticosteroids by up to 60%, leading to an increased risk of corticosteroid side effects. Co-administration of other strong CYP3A4 inhibitors (e.g., ritonavir,
atazanavir, clarithromycin, indinavir, itraconazole, nefazodone, nelfinavir, saquinavir, telithromycin, cobicistat-containing products) with Kenalog-40 Injection may cause increased plasma concentration of triamcinolone leading to adverse reactions. (See ADVERSE REACTIONS.) During postmarketing use, there have been reports of clinically significant drug interactions in patients receiving triamcinolone acetonide and strong CYP3A4 inhibitors (e.g., ritonavir). (See WARNINGS, Endocrine and PRECAUTIONS, Endocrine.) Consider the benefit-risk of concomitant use and monitor for systemic corticosteroid side effects.

Digitalis glycosides: Patients on digitalis glycosides may be at increased risk of arrhythmias due to hypokalemia.

Estrogens, including oral contraceptives: Estrogens may decrease the hepatic metabolism of certain corticosteroids, thereby increasing their effect.

Hepatic enzyme inducers (e.g., barbiturates, phenytoin, carbamazepine, rifampin): Drugs which induce hepatic microsomal drug metabolizing enzyme activity may enhance the metabolism of corticosteroids and require that the dosage of the corticosteroid be increased.

Nonsteroidal anti-inflammatory drugs (NSAIDs): Concomitant use of aspirin (or other nonsteroidal anti- inflammatory drugs) and corticosteroids increases the risk of gastrointestinal side effects. Aspirin should be used cautiously in conjunction with corticosteroids in hypoprothrombinemia. The clearance of salicylates may be increased with concurrent use of corticosteroids.

Skin tests: Corticosteroids may suppress reactions to skin tests.

Vaccines: Patients on prolonged corticosteroid therapy may exhibit a diminished response to toxoids and live or inactivated vaccines due to inhibition of antibody response. Corticosteroids may also potentiate the replication of some organisms contained in live attenuated vaccines. Routine administration of vaccines or toxoids should be deferred until corticosteroid therapy is discontinued if possible (see WARNINGS: Infections: Vaccination).

Carcinogenesis, Mutagenesis, Impairment of Fertility
No adequate studies have been conducted in animals to determine whether corticosteroids have a potential for carcinogenesis or mutagenesis.

Steroids may increase or decrease motility and number of spermatozoa in some patients.

Pregnancy

Teratogenic Effects
Corticosteroids have been shown to be teratogenic in many species when given in doses equivalent to the human dose. Animal studies in which corticosteroids have been given to pregnant mice, rats, and rabbits have yielded an increased incidence of cleft palate in the offspring. There are no adequate and well-controlled studies in pregnant women. Corticosteroids should be used during pregnancy only if the potential benefit justifies the potential risk to the fetus. Infants born to mothers who have received corticosteroids during pregnancy should be carefully observed for signs of hypoadrenalism.

Nursing Mothers
Systemically administered corticosteroids appear in human milk and could suppress growth, interfere with endogenous corticosteroid production, or cause other untoward effects. Caution should be exercised when corticosteroids are administered to a nursing woman.
Pediatric Use
This product contains benzyl alcohol as a preservative. Benzyl alcohol, a component of this product, has been associated with serious adverse events and death, particularly in pediatric patients. The “gasping syndrome” (characterized by central nervous system depression, metabolic acidosis, gasping
respirations, and high levels of benzyl alcohol and its metabolites found in the blood and urine) has been associated with benzyl alcohol dosages >99 mg/kg/day in neonates and low-birth-weight neonates. Additional symptoms may include gradual neurological deterioration, seizures, intracranial
hemorrhage, hematologic abnormalities, skin breakdown, hepatic and renal failure, hypotension, bradycardia, and cardiovascular collapse. Although normal therapeutic doses of this product deliver amounts of benzyl alcohol that are substantially lower than those reported in association with the “gasping syndrome,” the minimum amount of benzyl alcohol at which toxicity may occur is not known. Premature and low-birth- weight infants, as well as patients receiving high dosages, may be more likely to develop toxicity. Practitioners administering this and other medications containing benzyl alcohol should consider the combined daily metabolic load of benzyl alcohol from all sources.

The efficacy and safety of corticosteroids in the pediatric population are based on the well-established course of effect of corticosteroids which is similar in pediatric and adult populations. Published studies provide evidence of efficacy and safety in pediatric patients for the treatment of nephrotic syndrome (>2 years of age), and aggressive lymphomas and leukemias (>1 month of age). Other indications for pediatric use of corticosteroids, e.g., severe asthma and wheezing, are based on adequate and well-controlled trials conducted in adults, on the premises that the course of the diseases and their pathophysiology are considered to be substantially similar in both populations.

The adverse effects of corticosteroids in pediatric patients are similar to those in adults (see ADVERSE REACTIONS). Like adults, pediatric patients should be carefully observed with frequent measurements of blood pressure, weight, height, intraocular pressure, and clinical evaluation for the presence of infection, psychosocial disturbances, thromboembolism, peptic ulcers, cataracts, and osteoporosis. Pediatric patients who are treated with corticosteroids by any route, including systemically administered corticosteroids, may experience a decrease in their growth velocity. This negative impact of corticosteroids on growth has been observed at low systemic doses and in the absence of laboratory evidence of HPA axis suppression (i.e., cosyntropin stimulation and basal
cortisol plasma levels). Growth velocity may therefore be a more sensitive indicator of systemic corticosteroid exposure in pediatric patients than some commonly used tests of HPA axis function. The linear growth of pediatric patients treated with corticosteroids should be monitored, and the potential growth effects of prolonged treatment should be weighed against clinical benefits obtained and the availability of treatment alternatives. In order to minimize the potential growth effects of corticosteroids, pediatric patients should be titrated to the lowest effective dose.
Geriatric Use
No overall differences in safety or effectiveness were observed between elderly subjects and younger subjects, and other reported clinical experience has not identified differences in responses between the elderly and younger patients, but greater sensitivity of some older individuals cannot be ruled out.

ADVERSE REACTIONS

(listed alphabetically under each subsection)

The following adverse reactions may be associated with corticosteroid therapy:

Allergic reactions: Anaphylaxis including death, angioedema.
Cardiovascular: Bradycardia, cardiac arrest, cardiac arrhythmias, cardiac enlargement, circulatory collapse, congestive heart failure, fat embolism, hypertension, hypertrophic cardiomyopathy in premature infants, myocardial rupture following recent myocardial infarction (see WARNINGS), pulmonary edema, syncope, tachycardia, thromboembolism, thrombophlebitis, vasculitis.

Dermatologic: Acne, allergic dermatitis, cutaneous and subcutaneous atrophy, dry scaly skin, ecchymoses and petechiae, edema, erythema, hyperpigmentation, hypopigmentation, impaired wound healing, increased sweating, lupus erythematosus-like lesions, purpura, rash, sterile abscess, striae, suppressed reactions to skin tests, thin fragile skin, thinning scalp hair, urticaria.

Endocrine: Decreased carbohydrate and glucose tolerance, development of cushingoid state, glycosuria, hirsutism, hypertrichosis, increased requirements for insulin or oral hypoglycemic agents in diabetes, manifestations of latent diabetes mellitus, menstrual irregularities, postmenopausal vaginal hemorrhage, secondary adrenocortical and pituitary unresponsiveness (particularly in times of stress, as in trauma, surgery, or illness), suppression of growth in pediatric patients.

Fluid and electrolyte disturbances: Congestive heart failure in susceptible patients, fluid retention, hypokalemic alkalosis, potassium loss, sodium retention.

Gastrointestinal: Abdominal distention, bowel/bladder dysfunction (after intrathecal administration [see WARNINGS: Neurologic]), elevation in serum liver enzyme levels (usually reversible upon discontinuation), hepatomegaly, increased appetite, nausea, pancreatitis, peptic ulcer with possible perforation and hemorrhage, perforation of the small and large intestine (particularly in patients with inflammatory bowel disease), ulcerative esophagitis.

Metabolic: Negative nitrogen balance due to protein catabolism.

Musculoskeletal: Aseptic necrosis of femoral and humeral heads, calcinosis (following intra-articular or intralesional use), Charcot-like arthropathy, loss of muscle mass, muscle weakness, osteoporosis, pathologic fracture of long bones, post injection flare (following intra-articular use), steroid myopathy,
tendon rupture, vertebral compression fractures.

Neurologic/Psychiatric: Convulsions, depression, emotional instability, euphoria, headache, increased intracranial pressure with papilledema (pseudotumor cerebri) usually following discontinuation of treatment, insomnia, mood swings, neuritis, neuropathy, paresthesia, personality changes, psychiatric disorders, vertigo. Arachnoiditis, meningitis, paraparesis/paraplegia, and sensory disturbances have occurred after intrathecal administration. Spinal cord infarction, paraplegia, quadriplegia, cortical blindness, and stroke (including brainstem) have been reported after epidural administration of corticosteroids (see WARNINGS: Serious Neurologic Adverse Reactions with Epidural Administration and WARNINGS: Neurologic).

Ophthalmic: Exophthalmos, glaucoma, increased intraocular pressure, posterior subcapsular cataracts, rare instances of blindness associated with periocular injections.

Other: Abnormal fat deposits, decreased resistance to infection, hiccups, increased or decreased motility and number of spermatozoa, malaise, moon face, weight gain.

OVERDOSAGE

Treatment of acute overdosage is by supportive and symptomatic therapy. For chronic overdosage in the face of severe disease requiring continuous steroid therapy, the dosage of the corticosteroid may be reduced only temporarily, or alternate day treatment may be introduced.

DOSAGE AND ADMINISTRATION

General

NOTE: CONTAINS BENZYL ALCOHOL (see PRECAUTIONS).

The initial dose of Kenalog-40 Injection and Kenalog-80 Injection may vary from 2.5 mg to 100 mg per day depending on the specific disease entity being treated (see Dosage section below). However, in certain overwhelming, acute, life-threatening situations, administration in dosages exceeding the usual dosages may be justified and may be in multiples of the oral dosages.

IT SHOULD BE EMPHASIZED THAT DOSAGE REQUIREMENTS ARE VARIABLE AND MUST BE INDIVIDUALIZED ON THE BASIS OF THE DISEASE UNDER TREATMENT AND THE RESPONSE OF THE PATIENT. After a favorable response is noted, the proper maintenance dosage should be determined by decreasing the initial drug dosage in small decrements at appropriate time intervals until the lowest dosage which will maintain an adequate clinical response is reached. Situations which may make dosage adjustments necessary are changes in clinical status secondary to remissions or exacerbations in the disease process, the patient’s individual drug responsiveness, and the effect of patient exposure to stressful situations not directly related to the disease entity under treatment. In this latter situation it may be necessary to increase the dosage of the corticosteroid for a period of time consistent with the patient’s condition. If after long-term therapy the drug is to be stopped, it is recommended that it be withdrawn gradually rather than abruptly.

Dosage

SYSTEMIC

The suggested initial dose is 60 mg, injected deeply into the gluteal muscle. Atrophy of subcutaneous fat may occur if the injection is not properly given. Dosage is usually adjusted within the range of 40 mg to 80 mg, depending upon patient response and duration of relief. However, some patients may be well controlled on doses as low as 20 mg or less.

Hay fever or pollen asthma: Patients with hay fever or pollen asthma who are not responding to pollen administration and other conventional therapy may obtain a remission of symptoms lasting throughout the pollen season after a single injection of 40 mg to 100 mg.

In the treatment of acute exacerbations of multiple sclerosis, daily doses of 160 mg of triamcinolone for a week followed by 64 mg every other day for one month are recommended (see PRECAUTIONS: Neuro-Psychiatric).

In pediatric patients, the initial dose of triamcinolone may vary depending on the specific disease entity being treated. The range of initial doses is 0.11 mg/kg/day to 1.6 mg/kg/day in 3 or 4 divided doses (3.2 mg/m^2bsa/day to 48 mg/m^2bsa/day).

For the purpose of comparison, the following is the equivalent milligram dosage of the various glucocorticoids:

Cortisone, 25 | Triamcinolone, 4
Hydrocortisone, 20 | Paramethasone, 2
Prednisolone, 5 | Betamethasone, 0.75
Prednisone, 5 | Dexamethasone, 0.75
Methylprednisolone, 4

These dose relationships apply only to oral or intravenous administration of these compounds. When these substances or their derivatives are injected intramuscularly or into joint spaces, their relative properties may be greatly altered.
LOCAL

Intra-articular administration: A single local injection of triamcinolone acetonide is frequently sufficient, but several injections may be needed for adequate relief of symptoms.

Initial dose: 2.5 mg to 5 mg for smaller joints and from 5 mg to 15 mg for larger joints, depending on the specific disease entity being treated. For adults, doses up to 10 mg for smaller areas and up to 40 mg for larger areas have usually been sufficient. Single injections into several joints, up to a total of 80 mg, have been given.

Administration

GENERAL

STRICT ASEPTIC TECHNIQUE IS MANDATORY. The vial should be shaken before use to ensure a uniform suspension. Prior to withdrawal, the suspension should be inspected for clumping or granular appearance (agglomeration). An agglomerated product results from exposure to freezing temperatures and should not be used. After withdrawal, Kenalog-40 Injection and Kenalog-80 Injection should be injected without delay to prevent settling in the syringe. Careful technique should be employed to avoid the possibility of entering a blood vessel or introducing infection.

SYSTEMIC
For systemic therapy, injection should be made deeply into the gluteal muscle (see WARNINGS). For adults, a minimum needle length of 1½ inches is recommended. In obese patients, a longer needle may be required. Use alternative sites for subsequent injections.

LOCAL

For treatment of joints, the usual intra-articular injection technique should be followed. If an excessive amount of synovial fluid is present in the joint, some, but not all, should be aspirated to aid in the relief of pain and to prevent undue dilution of the steroid.

With intra-articular administration, prior use of a local anesthetic may often be desirable. Care should be taken with this kind of injection, particularly in the deltoid region, to avoid injecting the suspension into the tissues surrounding the site, since this may lead to tissue atrophy.

In treating acute nonspecific tenosynovitis, care should be taken to ensure that the injection of the corticosteroid is made into the tendon sheath rather than the tendon substance. Epicondylitis may be treated by infiltrating the preparation into the area of greatest tenderness.

STORAGE

Store at controlled room temperature, 20° to 25°C (68° to 77°F); protect from temperatures below 20°C (68°F).

Store vial in carton to protect from light.

Store vial upright.

HOW SUPPLIED

Kenalog®-40 Injection (triamcinolone acetonide injectable suspension, USP) is supplied in vials providing 40 mg triamcinolone acetonide per mL.

40 mg/mL, 1 mL vial | NDC 0003-0293-05
40 mg/mL, 5 mL vial | NDC 0003-0293-20
40 mg/mL, 10 mL vial | NDC 0003-0293-28

Kenalog®-80 Injection (triamcinolone acetonide injectable suspension, USP) is supplied in vials providing 80 mg triamcinolone acetonide per mL.

80 mg/mL, 1 mL vial | NDC 0003-0315-05
80 mg/mL, 5 mL vial | NDC 0003-0315-20

Bristol-Myers Squibb Company

Princeton, NJ 08543 USA

1374114A0

Revised: April 2019

POVIDONE-IODINE

APLICARE POVIDONE-IODINE TRIPLES- povidone-iodine solution

Aplicare Products, LLC

Disclaimer: Most OTC drugs are not reviewed and approved by FDA, however they may be marketed if they comply with applicable regulations and policies. FDA has not evaluated whether this product complies.

ACTIVE INGREDIENT

Povidone-iodine USP

PURPOSE

Antiseptic

USE

Antiseptic skin preparation

WARNINGS

Do not use

- if allergic to iodine
- in the eyes

For external use only

Avoid pooling beneath patient

Avoid excessive heat. Store at room temperature.

Ask a doctor before use if injuries are

- deep or puncture wounds
- serious burns

Stop use and ask a doctor if

- redness, irritation, swelling or pain persists or increases
- infection occurs

Keep out of reach of children.

In case of accidental ingestion, seek professional assistance or consult a poison control center immediately.

DIRECTIONS

Apply locally as needed

INACTIVE INGREDIENTS

- citric acid,
- disodium phosphate,
- nonoxynol-9,
- sodium hydroxide,
- water

OTHER INFORMATION

- 1% titratable iodine
- Not made with natural rubber latex
- For hospital or professional use only

Applicator is STERILE if Package is Intact

Manufactured by:

Aplicare Products, LLC,

550 Research Parkway

Meriden, CT 06450 USA

Made in USA

For questions or comments
800-633-5463

Revised: 12/2019

ALCOHOL PREP PAD

ALCOHOL PREP- isopropyl alcohol swab

Dynarex Corporation

Disclaimer: Most OTC drugs are not reviewed and approved by FDA, however they may be marketed if they comply with applicable regulations and policies. FDA has not evaluated whether this product complies.

ACTIVE INGREDIENT

Isopropyl Alcohol, 70 % v/v

PURPOSE

Antiseptic

USE

For preparation of the skin prior to injection.

WARNINGS

- For external use only
- Flammable, keep away from flame or fire
- Not for use with electrocautinary devices or procedures
- Do not use in eyes
- Sterile unless package is damaged or open.

Stop use and ask a doctor if:

- Irritation or redness develops
- Condition persists for more than 72 hours
- Cleansing of an injection site

Keep out of reach of children.

In case of accidental ingestion, seek professional assistance or consult a poison control center immediately.

DIRECTIONS

Wipe injection site vigorously and discard.

INACTIVE INGREDIENTS

- Water

OTHER INFORMATION

- Store at room temperature: 15 deg C to 30 deg C 59 deg F to 86 deg F
- Avoid excessive heat

Reorder No. 1113

Made in China

Manufactured for:

Dynarex Corporation

Orangeburg, NY 10962

www.dynarex.com

Revised: 11/2019

Sodium Chloride Injection, USP
0.9%

Fresenius Kabi USA, LLC

DESCRIPTION

Sodium Chloride Injection, USP, 0.9% is a sterile, nonpyrogenic solution. The osmolarity is 300 mOsmol per liter (calculated).

Each mL contains: Sodium chloride 9 mg; Water for Injection q.s. It contains no bacteriostat, antimicrobial agent or added buffer and is supplied only in single dose containers. Hydrochloric acid and/or sodium hydroxide may have been added for pH adjustment (pH 4.5-7.0).

Sodium chloride occurs as colorless cubic crystals or white crystalline powder and has a saline taste. Sodium chloride is freely soluble in water. It is soluble in glycerin and slightly soluble in alcohol.

The empirical formula for sodium chloride is NaCl and the molecular weight is 58.44.

CLINICAL PHARMACOLOGY

Sodium chloride in water dissociates to provide sodium (Na +) and chloride (Cl —) ions. These ions are normal constituents of the body fluids (principally extracellular) and are essential for maintaining electrolyte balance.

The distribution and excretion of sodium (Na +) and chloride (Cl —) are largely under the control of the kidney which maintains a balance between intake and output.

The small volume of fluid and amount of sodium chloride provided by Sodium Chloride Injection, USP, 0.9%, when used only as a vehicle for parenteral injection of drugs, is unlikely to exert a significant effect on fluid and electrolyte balance except possibly in very small infants.

Water is an essential constituent of all body tissues and accounts for approximately 70% of total body weight. Average normal adult daily requirement ranges from two to three liters (1 to 1.5 liters each for insensible water loss by perspiration and urine production).

Water balance is maintained by various regulatory mechanisms. Water distribution depends primarily on the concentration of electrolytes in the body compartments and sodium (Na +) plays a major role in maintaining physiologic equilibrium.

INDICATIONS AND USAGE

Sodium Chloride Injection, USP, 0.9% preparations are indicated for diluting or dissolving drugs for intramuscular, intravenous or subcutaneous injection according to instructions of the manufacturer of the drug to be administered.

Sodium Chloride Injection, USP, 0.9% is also indicated for use in flushing of intravenous catheters.

WARNINGS

For use in newborns, when a sodium chloride solution is required for preparation or diluting medications or in flushing intravenous catheters, only preservative free Sodium Chloride Injection, USP, 0.9% should be used.

PRECAUTIONS

General

Consult the manufacturer’s instructions for choice of vehicle, appropriate dilution or volume for dissolving the drugs to be injected, including the route and rate of injection. Inspect reconstituted (diluted or dissolved) drugs for clari y (if soluble) and freedom from unexpected precipitation or discoloration prior to administration.

Pregnancy

Pregnancy Category C—Animal reproduction studies have not been conducted with Sodium Chloride Injection, USP, 0.9%. It is also not known whether Sodium Chloride Injection can cause fetal harm when administered to a pregnant woman or can affect reproduction capacity. Sodium Chloride Injection, USP, 0.9% should be given to a pregnant woman only if clearly needed.

ADVERSE REACTIONS

Reactions which may occur because of this solution, added drugs or the technique of reconstitution or administration include febrile response, local tenderness, abscess, tissue necrosis or infection at the site of injection, venous thrombosis or phlebitis extending from the site of injection and extravasation.

If an adverse reaction does occur, discontinue the infusion, evaluate the patient, institute appropriate countermeasures and, if possible, retrieve and save the remainder of the unused vehicle for examination.

OVERDOSAGE

When used as a diluent, solvent or intravascular flushing solution, this parenteral preparation is unlikely to pose a threat of sodium chloride or fluid overload except possibly in very small infants. In the event these should occur, reevaluate the patient and institute appropriate corrective measures. (See
PRECAUTIONS and ADVERSE REACTIONS).

DOSAGE AND ADMINISTRATION

Before Sodium Chloride Injection, USP, 0.9% is used as a vehicle for the administration of a drug, specific references should be checked for any possible incompatibility with sodium chloride.

The volume of the preparation to be used for diluting or dissolving any drug for injection is dependent on the vehicle concentration, dose and route of administration as recommended by the manufacturer.

Sodium Chloride Injection, USP, 0.9% is also indicated for use in flushing intravenous catheters. Prior to and after administration of the medication, the intravenous catheter should be flushed in its entirety with Sodium Chloride Injection, USP, 0.9%. Use in accord with any warnings or precautions appropriate to the medication being administered.

Parenteral drug products should be inspected visually for particulate matter and discoloration prior to administration, whenever solution and container permit.

HOW SUPPLIED

Sodium Chloride Injection, USP, 0.9%, preservative free, is available as follows:

Product Code | Unit of Sale | Strength | Each
918602 | 63323-186-02 Trays of 25 | 0.9% (18 mg per 2 mL) (9 mg per mL) | NDC 63323-186-04 2 mL fill, in a 3 mL Single-Dose vial
918610 | 63323-186-10 Trays of 25 | 0.9% (90 mg per 10 mL) (9 mg per mL) | NDC 63323-186-01 10 mL Single-Dose vial
918620 | 63323-186-20 Trays of 25 | 0.9% (180 mg per 20 mL) (9 mg per mL) | NDC 63323-186-03 20 mL Single-Dose vial

Preservative Free. Discard unused portion.

Use only if solution is clear and seal intact.

Store at 20º to 25ºC (68º to 77ºF) [see USP Controlled Room Temperature].

Fresenius Kabi Logo

www.fresenius-kabi.com

45764E

Revised: October 2018

XYLOCAINE - lidocaine hydrochloride injection, solution

XYLOCAINE MPF- lidocaine hydrochloride injection, solution
XYLOCAINE - lidocaine hydrochloride injection, solution
XYLOCAINE MPF- lidocaine hydrochloride, epinephrine bitartrate injection, solution
XYLOCAINE - lidocaine hydrochloride, epinephrine bitartrate injection, solution

Fresenius Kabi USA, LLC

Xylocaine® (lidocaine HCl Injection, USP)
Xylocaine® (lidocaine HCl and epinephrine Injection, USP)

For Infiltration and Nerve Block

Rx only

DESCRIPTION

Xylocaine (lidocaine HCl) Injections are sterile, nonpyrogenic, aqueous solutions that contain a local anesthetic agent with or without epinephrine and are administered parenterally by injection. See INDICATIONS AND USAGE section for specific uses.

Xylocaine solutions contain lidocaine HCl, which is chemically designated as acetamide, 2-(diethylamino)-N-(2,6-dimethylphenyl)-, monohydrochloride and has the molecular wt. 270.8.

Lidocaine HCl (C14H22N2O • HCl) has the following structural formula:

Xylocaine MPF Structural Formula

Epinephrine is (-) -3, 4-Dihydroxy-α-[(methylamino) methyl] benzyl alcohol and has the molecular wt. 183.21.

Epinephrine (C9H13NO3) has the following structural formula:

Epinephrine Structural Formula

Dosage forms listed as Xylocaine-MPF indicate single dose solutions that are Methyl Paraben Free (MPF).

Xylocaine MPF is a sterile, nonpyrogenic, isotonic solution containing sodium chloride.

Xylocaine in multiple dose vials: Each mL also contains 1 mg methylparaben as antiseptic preservative.

The pH of these solutions is adjusted to approximately 6.5 (5.0 to 7.0) with sodium hydroxide and/or hydrochloric acid.

Xylocaine MPF with Epinephrine is a sterile, nonpyrogenic, isotonic solution containing sodium chloride. Each mL contains lidocaine hydrochloride and epinephrine, with 0.5 mg sodium metabisulfite as an antioxidant and 0.2 mg citric acid as a stabilizer.

Xylocaine with Epinephrine in multiple dose vials: Each mL also contains 1 mg methylparaben as antiseptic preservative.

The pH of these solutions is adjusted to a proximately 4.5 (3.3 to 5.5) with sodium hydroxide and/or hydrochloric acid. Filled under nitrogen.

CLINICAL PHARMACOLOGY

Mechanism of Action
Lidocaine HCl stabilizes the neuronal membrane by inhibiting the ionic fluxes required for the initiation and conduction of impulses thereby effecting local anesthetic action.

Hemodynamics
Excessive blood levels may cause changes in cardiac output, total peripheral resistance, and mean arterial pressure. With central neural blockade these changes may be attributable to block of autonomic fibers, a direct depressant effect of the local anesthetic agent on various components of the cardiovascular system, and/or the beta-adrenergic receptor stimulating action of epinephrine when present. The net effect is normally a modest hypotension when the recommended dosages are not exceeded.

Pharmacokinetics and Metabolism
Information derived from diverse formulations, concentrations and usages reveals that lidocaine HCl is completely absorbed following parenteral administration, its rate of absorption depending, for example, upon various factors such as the site of administration and the presence or absence of a
vasoconstrictor agent. Except for intravascular administration, the highest blood levels are obtained following intercostal nerve block and the lowest after subcutaneous administration.

The plasma binding of lidocaine HCl is dependent on drug concentration, and the fraction bound decreases with increasing concentration. At concentrations of 1 to 4 mcg of free base per mL 60 to 80 percent of lidocaine HCl is protein bound. Binding is also dependent on the plasma concentration of the alpha-1-acid glycoprotein.

Lidocaine HCl crosses the blood-brain and placental barriers, presumably by passive diffusion.

Lidocaine HCl is metabolized rapidly by the liver, and metabolites and unchanged drug are excreted by the kidneys. Biotransformation includes oxidative N-dealkylation, ring hydroxylation, cleavage of the amide linkage, and conjugation. N-dealkylation, a major pathway of biotransformation, yields the metabolites monoethylglycinexylidide and glycinexylidide. The pharmacological/toxicological actions of these metabolites are similar to, but less potent than,
those of lidocaine HCl. Approximately 90% of lidocaine HCl administered is excreted in the form of various metabolites, and less than 10% is excreted unchanged. The primary metabolite in urine is a conjugate of 4-hydroxy-2,6-dimethylaniline.

The elimination half-life of lidocaine HCl following an intravenous bolus injection is typically 1.5 to 2 hours. Because of the rapid rate at which lidocaine HCl is metabolized, any condition that affects liver function may alter lidocaine HCl kinetics. The half-life may be prolonged two-fold or more in patients with liver dysfunction. Renal dysfunction does not affect lidocaine HCl kinetics but may increase the accumulation of metabolites.

Factors such as acidosis and the use of CNS stimulants and depressants affect the CNS levels of lidocaine HCl required to produce overt systemic effects. Objective adverse manifestations become increasingly apparent with increasing venous plasma levels above 6 mcg free base per mL. In the rhesus monkey arterial blood levels of 18 to 21 mcg/mL have been shown to be threshold for convulsive activity.

INDICATIONS AND USAGE

Xylocaine (lidocaine HCl) Injections are indicated for production of local or regional anesthesia by infiltration techniques such as percutaneous injection and intravenous regional anesthesia by peripheral nerve block techniques such as brachial plexus and intercostal and by central neural techniques such as lumbar and caudal epidural blocks, when the accepted procedures for these techniques as described in standard textbooks are observed.

CONTRAINDICATIONS

Lidocaine HCl is contraindicated in patients with a known history of hypersensitivity to local anesthetics of the amide type.

WARNINGS

XYLOCAINE INJECTIONS FOR INFILTRATION AND NERVE BLOCK SHOULD BE EMPLOYED ONLY BY CLINICIANS WHO ARE WELL VERSED IN DIAGNOSIS AND MANAGEMENT OF DOSE-RELATED TOXICITY AND OTHER ACUTE EMERGENCIES THAT MIGHT ARISE FROM THE BLOCK TO BE EMPLOYED AND THEN ONLY AFTER ENSURING THE IMMEDIATE AVAILABILITY OF OXYGEN, OTHER RESUSCITATIVE DRUGS, CARDIOPULMONARY EQUIPMENT AND THE PERSONNEL NEEDED FOR PROPER MANAGEMENT OF TOXIC REACTIONS AND RELATED EMERGENCIES (see also ADVERSE REACTIONS and PRECAUTIONS). DELAY IN PROPER MANAGEMENT OF DOSE-RELATED TOXICITY,
UNDERVENTILATION FROM ANY CAUSE AND/OR ALTERED SENSITIVITY MAY LEAD TO THE DEVELOPMENT OF ACIDOSIS, CARDIAC ARREST AND, POSSIBLY, DEATH.

Methemoglobinemia
Cases of methemoglobinemia have been reported in association with local anesthetic use. Although all patients are at risk for methemoglobinemia, patients with glucose-6-phosphate dehydrogenase deficiency, congenital or idiopathic methemoglobinemia, cardiac or pulmonary compromise, infants under 6 months of age, and concurrent exposure to oxidizing agents or their metabolites are more susceptible to developing clinical manifestations of the condition. If local anesthetics must be used in these patients, close monitoring for symptoms and signs of methemoglobinemia is recommended.

Signs of methemoglobinemia may occur immediately or may be delayed some hours after exposure, and are characterized by a cyanotic skin discoloration and/or abnormal coloration of the blood. Methemoglobin levels may continue to rise; therefore, immediate treatment is required to avert more serious central nervous system and cardiovascular adverse effects, including seizures, coma, arrhythmias, and death. Discontinue Xylocaine and any other oxidizing agents. Depending on the severity of the signs and symptoms, patients may respond to supportive care, i.e., oxygen therapy, hydration. A more severe clinical presentation may require treatment with methylene blue, exchange transfusion, or hyperbaric oxygen.

Intra-articular infusions of local anesthetics following arthroscopic and other surgical procedures is an unapproved use, and there have been post-marketing reports of chondrolysis in patients receiving such infusions. The majority of reported cases of chondrolysis have involved the shoulder joint; cases of gleno-humeral chondrolysis have been described in pediatric and adult patients following intra-articular infusions of local anesthetics with and without epinephrine for periods of 48 to 72 hours. There is insufficient information to determine whether shorter infusion periods are not associated with these findings. The time of onset of symptoms, such as joint pain, stiffness and loss of motion can be variable, but may begin as early as the 2nd month after surgery. Currently, there is no effective treatment for chondrolysis; patients who experienced chondrolysis have required additional diagnostic and therapeutic procedures and some required arthroplasty or shoulder replacement.

To avoid intravascular injection, aspiration should be performed before the local anesthetic solution is injected. The needle must be repositioned until no return of blood can be elicited by aspiration. Note, however, that he absence of blood in the syringe does not guarantee that intravascular injection has
been avoided.

Local anesthetic solutions containing antimicrobial preservatives (e.g., methylparaben) should not be used for epidural or spinal anesthesia because the safety of these agents has not been established with regard to intrathecal injection, either intentional or accidental. Xylocaine with epinephrine solutions contain sodium metabisulfite, a sulfite that may cause allergic- type reactions including anaphylactic symptoms and life-threatening or less severe
asthmatic episodes in certain susceptible people. The overall prevalence of sulfite sensitivity in the general population is unknown and probably low. Sulfite sensitivity is seen more frequently in asthmatic than in non-asthmatic people.

Anaphylactic reactions may occur following administration of lidocaine hydrochloride (see ADVERSE REACTIONS).

In the case of severe reaction, discontinue the use of the drug.

PRECAUTIONS

General
The safety and effectiveness of lidocaine HCl depend on proper dosage, correct technique, adequate precautions, and readiness for emergencies. Standard textbooks should be consulted for specific techniques and precautions for various regional anesthetic procedures.

Resuscitative equipment, oxygen, and other resuscitative drugs should be available for immediate use (see WARNINGS and ADVERSE REACTIONS). The lowest dosage that results in effective anesthesia should be used to avoid high plasma levels and serious adverse effects. Syringe aspirations should also be performed before and during each supplemental injection when using indwelling catheter techniques. During the administration of epidural anesthesia, it is recommended that a test dose be administered initially and that the patient be monitored for central nervous system toxicity and cardiovascular toxicity, as well as for signs of unintended intrathecal administration, before proceeding. When clinical conditions permit, consideration should be given to employing local
anesthetic solutions that contain epinephrine for the test dose because circulatory changes compatible with epinephrine may also serve as a warning sign of unintended intravascular injection. An intravascular injection is still possible even if aspirations for blood are negative. Repeated doses of lidocaine HCl may cause significant increases in blood levels with each repeated dose because of slow accumulation of the drug or its metabolites. Tolerance to elevated blood
levels varies with the status of the patient. Debilitated, elderly patients, acutely ill patients, and children should be given reduced doses commensurate with their age and physical condition. Lidocaine HCl should also be used with caution in patients with severe shock or heart block.

Lumbar and caudal epidural anesthesia should be used with extreme caution in persons with the following conditions: existing neurological disease, spinal deformities, septicemia, and severe hypertension.

Local anesthetic solutions containing a vasoconstrictor should be used cautiously and in carefully circumscribed quantities in areas of the body supplied by end arteries or having otherwise compromised blood supply. Patients with peripheral vascular disease and those with hypertensive vascular disease may exhibit exaggerated vasoconstrictor response. Ischemic injury or necrosis may result. Preparations containing a vasoconstrictor should be used with caution in patients during or following the administration of potent general anesthetic agents, since cardiac arrhythmias may occur under such conditions.

Careful and constant monitoring of cardiovascular and respiratory (adequacy of ventilation) vital signs and the patient’s state of consciousness should be accomplished after each local anesthetic injection. It should be kept in mind at such times that restlessness, anxiety, tinnitus, dizziness, blurred vision, tremors, depression or drowsiness may be early warning signs of central nervous system toxicity.

Since amide-type local anesthetics are metabolized by the liver, Xylocaine Injection should be used with caution in patients with hepatic disease. Patients with severe hepatic disease, because of their inability to metabolize local anesthetics normally, are at greater risk of developing toxic plasma concentrations. Xylocaine Injection should also be used with caution in patients with impaired cardiovascular function since they may be less able to compensate for functional changes associated with the prolongation of A-V conduction produced by these drugs.

Many drugs used during the conduct of anesthesia are considered potential triggering agents for familial malignant hyperthermia. Since it is not known whether amide-type local anesthetics may trigger this reaction and since the need for supplemental general anesthesia cannot be predicted in advance, it is suggested that a standard protocol for the management of malignant hyperthermia should be available. Early unexplained signs of tachycardia, tachypnea, labile blood pressure and metabolic acidosis may precede temperature elevation. Successful outcome is dependent on early diagnosis, prompt discontinuance of the suspect triggering agent(s) and institution of treatment, including oxygen therapy, indicated supportive measures and dantrolene (consult dantrolene sodium intravenous package insert before using).

Proper tourniquet technique, as described in publications and standard textbooks, is essential in the performance of intravenous regional anesthesia. Solutions containing epinephrine or other vasoconstrictors should not be used for this technique.Lidocaine HCl should be used with caution in persons with known drug sensitivities. Patients allergic to para-aminobenzoic acid derivatives (procaine, tetracaine, benzocaine, etc.) have not shown cross-sensitivity to lidocaine HCl.

Use in the Head and Neck Area

Small doses of local anesthetics injected into the head and neck area, including retrobulbar, dental and stellate ganglion blocks, may produce adverse reactions similar to systemic toxicity seen with unintentional intravascular injections of larger doses. Confusion, convulsions, respiratory depression and/or respiratory arrest, and cardiovascular stimulation or depression have been reported. These reactions may be due to intra-arterial injection of the local anesthetic with retrograde flow to the cerebral circulation. Patients receiving these blocks should have their circulation and respiration monitored and be constantly observed. Resuscitative equipment and personnel for treating adverse reactions should be immediately available. Dosage recommendations
should not be exceeded (see DOSAGE AND ADMINISTRATION).

Information for Patients

When appropriate, patients should be informed in advance that they may experience temporary loss of sensation and motor activity, usually in the lower half of the body, following proper administration of epidural anesthesia.

Inform patients that use of local anesthetics may cause methemoglobinemia, a serious condition that must be treated promptly. Advise patients or caregivers to seek immediate medical attention if they or someone in their care experience the following signs or symptoms: pale, gray, or blue colored skin (cyanosis); headache; rapid heart rate; shortness of breath; lightheadedness; or fatigue.

Clinically Significant Drug Interactions

The administration of local anesthetic solutions containing epinephrine or norepinephrine to patients receiving monoamine oxidase inhibitors or tricyclic antidepressants may produce severe, prolonged hypertension.

Phenothiazines and butyrophenones may reduce or reverse the pressor effect of epinephrine.

Concurrent use of these agents should generally be avoided. In situations when concurrent therapy is necessary, careful patient monitoring is essential.
Concurrent administration of vasopressor drugs (for the treatment of hypotension related to obstetric blocks) an ergot-type oxytocic drugs may cause severe, persistent hypertension or cerebrovascular accidents.

Drug/Laboratory Test Interactions
The intramuscular injection of lidocaine HCl may result in an increase in creatine phosphokinase levels. Thus, the use of this enzyme determination, without isoenzyme separation, as a diagnostic test for the presence of acute myocardial infarction may be compromised by the intramuscular injection of lidocaine HCl.

Patients who are administered local anesthetics are at increased risk of developing methemoglobinemia when concurrently exposed to the following drugs, which could include other local anesthetics:

Examples of Drugs Associated with Methemoglobinemia:

Class | Examples
Nitrates/Nitrites | nitric oxide, nitroglycerin, nitroprusside, nitrous oxide
Local anesthetics | articaine, benzocaine, bupivacaine, lidocaine, mepivacaine, prilocaine, procaine, ropivacaine, tetracaine
Antineoplastic agents | cyclophosphamide, flutamide, hydroxyurea, ifosfamide, rasburicase
Antibiotics | dapsone, nitrofurantoin, paraaminosalicylic acid, sulfonamides
Antimalarials | chloroquine, primaquine
Anticonvulsants | phenobarbital, phenytoin, sodium valproate
Other drugs | acetaminophen, metoclopramide, quinine, sulfasalazine

Carcinogenesis, Mutagenesis, Impairment of Fertility
Studies of lidocaine HCl in anima s to evaluate the carcinogenic and mutagenic potential or the effect on fertility have not been conducted.

Pregnancy

Teratogenic Effects: Pregnancy Category B.

Reproduction studies have been performed in rats at doses up to 6.6 times the human dose and have revealed no evidence of harm to the fetus caused by lidocaine HCl. There are, however, no adequate and well-controlled studies in pregnant women. Animal reproduction studies are not always predictive of human response. General consideration should be given to this fact before administering lidocaine HCl to women of childbearing potential, especially during early pregnancy when maximum organogenesis takes place.

Labor and Delivery
Local anesthetics rapidly cross the placenta and when used for epidural, paracervical, pudendal or caudal block anesthesia, can cause varying degrees of maternal, fetal and neonatal toxicity (see CLINICAL PHARMACOLOGY, Pharmacokinetics and Metabolism). The potential for toxicity depends upon
the procedure performed, the type and amount of drug used, and the technique of drug administration. Adverse reactions in the parturient, fetus and neonate involve alterations of the central nervous system, peripheral vascular tone and cardiac function.

Maternal hypotension has resulted from regional anesthesia. Local anesthetics produce vasodilation by blocking sympathetic nerves. Elevating the patient’s legs and positioning her on her left side will help prevent decreases in blood pressure.

The fetal heart rate also should be monitored continuously, and electronic fetal monitoring is highly advisable.

Epidural, spinal, paracervical, or pudendal anesthesia may alter the forces of parturition through changes in uterine contractility or maternal expulsive efforts. In one study, paracervical block anesthesia was associated with a decrease in the mean duration of first stage labor and facilitation of cervical dilation. However, spinal and epidural anesthesia have also been reported to prolong the second stage of labor by removing the parturient’s reflex urge to bear down or by interfering with motor function. The use of obstetrical anesthesia may increase the need for forceps assistance.

The use of some local anesthetic drug products during labor and delivery may be followed by diminished muscle strength and tone for the first day or two of life. The long-term significance of these observations is unknown. Fetal bradycardia may occur in 20 to 30 percent of patients receiving paracervical nerve block anesthesia with the amide-type local anesthetics and may be associated with fetal acidosis. Fetal heart rate should always be monitored during paracervical anesthesia. The physician should weigh the possible advantages against risks when considering a paracervical block in prematurity, toxemia of pregnancy, and fetal distress. Careful adherence to recommended dosage is of the utmost importance in obstetrical paracervical block. Failure to achieve adequate analgesia with recommended doses should arouse suspicion of intravascular or fetal intracranial injection. Cases compatible with unintended fetal intracranial injection of local anesthetic solution have been reported following intended paracervical or pudendal block or both. Babies so affected present with unexplained neonatal depression at birth, which correlates with high local anesthetic serum levels, and often manifest seizures within six hours. Prompt use of supportive measures combined with forced urinary excretion of the local anesthetic has been used successfully to manage this complication.

Case reports of maternal convulsions and cardiovascular collapse following use of some local anesthetics for paracervical block in early pregnancy (as anesthesia for elective abortion) suggest that systemic absorption under these circumstances may be rapid. The recommended maximum dose of each drug should not be exceeded. Injection should be made slowly and with frequent aspiration. Allow a 5-minute interval between sides.

Nursing Mothers
It is not known whether this drug is excreted in human milk. Because many drugs are excreted in human milk, caution should be exercised when lidocaine HCl is administered to a nursing woman.

Pediatric Use
Dosages in children should be reduced, commensurate with age, body weight and physical condition (see DOSAGE AND ADMINISTRATION).

ADVERSE REACTIONS

Systemic
Adverse experiences following the administration of lidocaine HCl are similar in nature to those observed with other amide local anesthetic agents. These adverse experiences are, in general, dose- related and may result from high plasma levels caused by excessive dosage, rapid absorption or inadvertent intravascular injection, or may result from a hypersensitivity, idiosyncrasy or diminished tolerance on the part of the patient. Serious adverse experiences are generally systemic in nature. The following types are those most commonly reported:

Central Nervous System

CNS manifestations are excitatory and/or depressant and may be characterized by lightheadedness, nervousness, apprehension, euphoria, confusion, dizziness, drowsiness, tinnitus, blurred or double vision, vomiting, sensations of heat, cold or numbness, twitching, tremors, convulsions, unconsciousness, respiratory depression and arrest. The excitatory manifestations may be very brief or may not occur at all, in which case the first manifestation of toxicity may be drowsiness merging into unconsciousness and respiratory arrest.

Drowsiness following the administration of lidocaine HCl is usually an early sign of a high blood level of the drug and may occur as a consequence of rapid absorption.

Cardiovascular System
Cardiovascular manifestations are usually depressant and are characterized by bradycardia, hypotension, and cardiovascular collapse, which may lead to cardiac arrest.

Allergic

Allergic reactions are characterized by cutaneous lesions, urticaria, edema or anaphylactoid reactions. Allergic reactions may occur as a result of sensitivity either to local anesthetic agents or to the methylparaben used as a preservative in the multiple dose vials. Allergic reactions, including anaphylactic reactions, may occur as a result of sensitivity to lidocaine, but are infrequent. If allergic reactions do occur, they should be managed by conventional means. The detection of sensitivity by skin testing is of doubtful value.

There have been no reports of cross sensitivity between lidocaine hydrochloride and procainamide or between lidocaine hydrochloride and quinidine.
Neurologic
The incidences of adverse reactions associated with the use of local anesthetics may be related to the total dose of local anesthetic administered and are also dependent upon the particular drug used, the route of administration and the physical status of the patient. In a prospective review of 10,440 patients who received lidocaine HCl for spinal anesthesia, the incidences of adverse reactions were reported to be about 3 percent each for positional headaches, hypotension and backache; 2 percent for shivering; and less than 1 percent each for peripheral nerve symptoms, nausea, respiratory inadequacy and double vision. Many of these observations may be related to local anesthetic techniques, with or without a contribution from the local anesthetic.

In the practice of caudal or lumbar epidural block, occasional unintentional penetration of the subarachnoid space by the catheter may occur. Subsequent adverse effects may depend partially on the amount of drug administered subdurally. These may include spinal block of varying magnitude (including total spinal block), hypotension secondary to spinal block, loss of bladder and bowel control, and loss of perineal sensation and sexual function. Persistent motor, sensory and/or autonomic (sphincter control) deficit of some lower spinal segments with slow recovery (several months) or incomplete recovery have been reported in rare instances when caudal or lumbar epidural block has been attempted. Backache and headache have also been noted following use of these
anesthetic procedures.

There have been reported cases of permanent injury to extraocular muscles requiring surgical repair following retrobulbar administration.

Hematologic

Methemoglobinemia

OVERDOSAGE

Acute emergencies from local anesthetics are generally related to high plasma levels encountered during therapeutic use of local anesthetics or to unintended subarachnoid injection of local anesthetic solution (see ADVERSE REACTIONS, WARNINGS, and PRECAUTIONS).

Management of Local Anesthetic Emergencies

The first consideration is prevention, best accomplished by careful and constant monitoring of cardiovascular and respiratory vital signs and the patient’s state of consciousness after each local anesthetic injection. At the first sign of change, oxygen should be administered.

The first step in the management of convulsions, as well as underventilation or apnea due to unintended subarachnoid injection of drug solution, consists of immediate attention to the maintenance of a patent airway and assisted or controlled ventilation with oxygen and a delivery system capable of permitting immediate positive airway pressure by mask. Immediately after the institution of these ventilatory measures, the adequacy of the circulation should be evaluated, keeping in mind that drugs used to treat convulsions sometimes depress the circulation when administered intravenously. Should convulsions persist despite adequate respiratory support, and if the status of the circulation permits, small increments of an ultra-short acting barbiturate (such as thiopental or thiamylal) or a benzodiazepine (such as diazepam) may be administered intravenously. The clinician should be familiar, prior to the use of local anesthetics, with these anticonvulsant drugs. Supportive treatment of circulatory depression may require administration of intravenous fluids and, when appropriate, a vasopressor as directed by the clinical situation (e.g., ephedrine).

If not treated immediately, both convulsions and cardiovascular depression can result in hypoxia, acidosis, bradycardia, arrhythmias and cardiac arrest. Underventilation or apnea due to unintentional subarachnoid injection of local anesthetic solution may produce these same signs and also lead to cardiac arrest if ventilatory support is not instituted. If cardiac arrest should occur, standard cardiopulmonary resuscitative measures should be instituted.

Endotracheal intubation, employing drugs and techniques familiar to the clinician, may be indicated, after initial administration of oxygen by mask, if difficulty is encountered in the maintenance of a patent airway or if prolonged ventilatory support (assisted or controlled) is indicated.

Dialysis is of negligible value in the treatment of acute overdosage with lidocaine HCl.

The oral LD50 of lidocaine HCl in non-fasted female rats is 459 (346 to 773) mg/kg (as the salt) and 214 (159 to 324) mg/kg (as the salt) in fasted female rats.

DOSAGE AND ADMINISTRATION

Table 1 (Recommended Dosages) summarizes the recommended volumes and concentrations of Xylocaine Injection for various types of anesthetic procedures. The dosages suggested in this table are for normal healthy adults and refer to the use of epinephrine-free solutions. When larger volumes are required, only solutions containing epinephrine should be used except in those cases where vasopressor drugs may be contraindicated.

There have been adverse event reports of chondrolysis in patients receiving intra-articular infusions of local anesthetics following arthroscopic and other surgical procedures. Xylocaine is not approved for this use (see WARNINGS and DOSAGE AND ADMINISTRATION).

These recommended doses serve only as a guide to the amount of anesthetic required for most routine procedures. The actual volumes and concentrations to be used depend on a number of factors such as type and extent of surgical procedure, depth of anesthesia and degree of muscular relaxation required, duration of anesthesia required, and the physical condition of the patient. In all cases the lowest concentration and smallest dose that will produce the desired result should be given. Dosages should be reduced for children and for the elderly and debilitated patients and patients with cardiac and/or liver disease.

The onset of anesthesia, the duration of anesthesia and the degree of muscular relaxation are proportional to the volume and concentration (i.e., total dose) of local anesthetic used. Thus, an increase in volume and concentration of Xylocaine Injection will decrease the onset of anesthesia, prolong the duration of anesthesia, provide a greater degree of muscular relaxation and increase the segmental spread of anesthesia. However, increasing the volume and concentration of Xylocaine Injection may result in a more profound fall in blood pressure when used in epidural anesthesia. Although the incidence of side effects with lidocaine HCl is quite low, caution should be exercised when employing large volumes and concentrations, since the incidence of side effects is directly proportional to the total dose of local anesthetic agent injected.

For intravenous regional anesthesia, only the 50 mL single dose vial containing Xylocaine (lidocaine HCl) 0.5% Injection should be used.

Epidural Anesthesia

For epidural anesthesia, only the following dosage forms Xylocaine Injection are recommended:

1% without epinephrine | 10 mL Plastic Ampule
1% without epinephrine | 30 mL single dose solutions
1% with epinephrine 1:200,000 | 30 mL single dose solutions
1.5% without epinephrine | 10 mL Plastic Ampule
1.5% without epinephrine | 20 mL Plastic Ampule
1.5% with epinephrine 1:200,000 | 30 mL ampules, 30 mL single dose solutions
2% without epinephrine | 10 mL Plastic Ampule
2% with epinephrine 1:200,000 | 20 mL ampules, 20 mL single dose solutions

Although these solutions are intended specifically for epidural anesthesia, they may also be used for infiltration and peripheral nerve block, provided they are employed as single dose units. These solutions contain no bacteriostatic agent.

In epidural anesthesia, the dosage varies with the number of dermatomes to be anesthetized (generally 2 to 3 mL of the indicated concentration per dermatome).
Caudal and Lumbar Epidural Block

As a precaution against the adverse experience sometimes observed following unintentional penetration of the subarachnoid space, a test dose such as 2 to 3 mL of 1.5% lidocaine HCl should be administered at least 5 minutes prior to injecting the total volume required for a lumbar or caudal epidural block. The test dose should be repeated if the patient is moved in a manner that may have displaced the catheter. Epinephrine, if contained in the test dose (10 to 15 mcg have been suggested), may serve as a warning of unintentional intravascular injection. If injected into a blood vessel, this amount of epinephrine is likely to produce a transient “epinephrine response” within 45 seconds, consisting of an increase in heart rate and systolic blood pressure, circumoral pallor, palpitations and nervousness in the unsedated patient. The sedated patient may exhibit only a pulse rate increase of 20 or more beats per minute for 15 or
more seconds. Patients on beta blockers may not manifest changes in heart rate, but blood pressure monitoring can detect an evanescent rise in systolic blood pressure. Adequate time should be allowed for onset of anesthesia after administration of each test dose. The rapid injection of a large volume of Xylocaine Injection through the catheter should be avoided, and, when feasible, fractional doses should be administered.

In the event of the known injection of a large volume of local anesthetic solution into the subarachnoid space, after suitable resuscitation and if the catheter is in place, consider attempting the recovery of drug by draining a moderate amount of cerebrospinal fluid (such as 10 mL) through the epidural catheter.
MAXIMUM RECOMMENDED DOSAGES

Adults

For normal healthy adults, the individual maximum recommended dose of lidocaine HCl with epinephrine should not exceed 7 mg/kg (3.5 mg/lb) of body weight, and in general it is recommended that the maximum total dose not exceed 500 mg. When used without epinephrine the maximum individual dose should not exceed 4.5 mg/kg (2 mg/lb) of body weight, and in general it is recommended that the maximum total dose does not exceed 300 mg. For continuous epidural or caudal anesthesia, the maximum recommended dosage should not be administered at intervals of less than 90 minutes. When continuous lumbar or caudal epidural anesthesia is used for non-obstetrical procedures, more drug may be administered if required to produce adequate anesthesia.

The maximum recommended dose per 90 minute period of lidocaine hydrochloride for paracervical block in obstetrical patients and non-obstetrical patients is 200 mg total. One half of the total dose is usually administered to each side. Inject slowly, five minutes between sides (see also discussion of paracervical block in PRECAUTIONS).

For intravenous regional anesthesia, the dose administered should not exceed 4 mg/kg in adults.

Children

It is difficult to recommend a maximum dose of any drug for children, since this varies as a function of age and weight. For children over 3 years of age who have a normal lean body mass and normal body development, the maximum dose is determined by the child’s age and weight. For example, in a child of 5 years weighing 50 lbs the dose of lidocaine HCl should not exceed 75 to 100 mg (1.5 to 2 mg/lb). The use of even more dilute solutions (i.e., 0.25 to 0.5%) and total dosages not to exceed 3 mg/kg (1.4 mg/lb) are recommended for induction of intravenous regional anesthesia in children.

In order to guard against systemic toxicity, the lowest effective concentration and lowest effective dose should be used at all times. In some cases it will be necessary to dilute available concentrations with 0.9% sodium chloride injection in order to obtain the required final concentration.

NOTE: Parenteral drug products should be inspected visually for particulate matter and discoloration prior to administration whenever the solution and container permit. The Injection is not to be used if its color is pinkish or darker than slightly yellow or if it contains a precipitate.

Table 1: Recommended Dosages

Procedure | Xylocaine (lidocaine hydrochloride); Injection (without epinephrine)
Procedure | Conc (%) | Vol (mL) | Total Dose (mg)
Infiltration
Percutaneous | 0.5 or 1 | 1 to 60 | 5 to 300
Intravenous regional | 0.5 | 10 to 60 | 50 to 300
Peripheral Nerve Blocks, e.g.,
Brachial | 1.5 | 15 to 20 | 225 to 300
Dental | 2 | 1 to 5 | 20 to 100
Intercostal | 1 | 3 | 30
Paravertebral | 1 | 3 to 5 | 30 to 50
Pundendal (each side) | 1 | 10 | 100
Paracervical
Obstetrical analgesia
(each side) | 1 | 10 | 100
Sympathetic Nerve Blocks, e.g.,
Cervical (stellate ganglion) | 1 | 5 | 50
Lumbar | 1 | 5 to 10 | 50 to 100
Central Neural Blocks
Epidural *
Thoracic | 1 | 20 to 30 | 200 to 300
Lumbar
Analgesia | 1 | 25 to 30 | 250 to 300
Anesthesia | 1.5 | 15 to 20 | 225 to 300
 | 2 | 10 to 15 | 200 to 300
Caudal
Obstetrical analgesia | 1 | 20 to 30 | 200 to 300
Surgical anesthesia | 1.5 | 15 to 20 | 225 to 300

*Dose determined by number of dermatomes to be anesthetized (2 to 3 mL/dermatome).

THE ABOVE SUGGESTED CONCENTRATIONS AND VOLUMES SERVE ONLY AS A GUIDE. OTHER VOLUMES AND CONCENTRATIONS MAY BE USED PROVIDED THE TOTAL MAXIMUM RECOMMENDED DOSE IS NOT EXCEEDED.

STERILIZATION, STORAGE AND TECHNICALPROCEDURES

Disinfecting agents containing heavy metals, which cause release of respective ions (mercury, zinc, copper, etc) should not be used for skin or mucous membrane disinfection as they have been related to incidents of swelling and edema. When chemical disinfection of multi-dose vials is desired, either isopropyl alcohol (91%) or ethyl alcohol (70%) is recommended. Many commercially available brands of rubbing alcohol, as well as solutions of ethyl alcohol not of USP grade, contain denaturants which are injurious to rubber and therefore are not to be used.

Dosage forms listed as Xylocaine-MPF indicate single dose solutions that are Methyl Paraben Free (MPF).

HOW SUPPLIED

Xylocaine® (lidocaine HCl Injection, USP)

Product Code | Unit of Sale | Strength | Each
480457 | NDC 63323-484-57 Unit of 25 | 0.5% (250 mg per 50 mL) (5 mg per mL) | NDC 63323-484-57 50 mL Multiple Dose Vial
480527 | NDC 63323-485-27 Unit of 25 | 1% (200 mg per 20 mL) (10 mg per mL) | NDC 63323-485-01 20 mL Multiple Dose Vial
480557 | NDC 63323-485-57 Unit of 25 | 1% (500 mg per 50 mL) (10 mg per mL) | NDC 63323-485-03 50 mL Multiple Dose Vial
480617 | NDC 63323-486-17 Unit of 25 | 2% (200 mg per 10 mL) (20 mg per mL) | NDC 63323-486-01 10 mL Multiple Dose Vial
480627 | NDC 63323-486-27 Unit of 25 | 2% (400 mg per 20 mL) (20 mg per mL) | NDC 63323-486-02 20 mL Multiple Dose Vial
480657 | NDC 63323-486-57 Unit of 25 | 2% (1,000 mg per 5 mL) (20 mg per mL) | NDC 63323-486-05 50 mL Multiple Dose Vial

Xylocaine®-MPF (lidocaine HCl Injection, USP)

Product Code | Unit of Sale | Strength | Each
491157 | NDC 63323-491-57 Unit of 25 | 0.5% (250 mg per 50 mL) (5 mg per mL) | NDC 63323-491-01 50 mL Single Dose Vial
491227 | NDC 63323-492-27 Unit of 25 | 1% (20 mg per 2 mL (10 mg per mL) | NDC 63323-492-04 2 mL Single Dose Vial
491257 | NDC 63323-492-57 Unit of 25 | 1% (50 mg per 5 mL (10 mg per mL) | NDC 63323-492-09 5 mL Single Dose Vial
491297 | NDC 63323-492-97 Unit of 5 | 1% (100 mg per 10 mL) (10 mg per mL) | NDC 63323-492-08 10 mL Plastic Ampule
491237 | NDC 63323-492-37 Unit of 25 | 1% (300 mg per 30 mL) (10 mg per mL) | NDC 63323-492-07 30 mL Single Dose Vial
491231 | NDC 63323-492-31 Unit of 5 | 1% (300 mg per 30 mL) (10 mg per mL) | NDC 63323-492-03 30 mL Single Dose Vial
491397 | NDC 63323-493-97 Unit of 5 | 1.5% (150 mg per 10 mL) (15 mg per mL) | NDC 63323-493-03 10 mL Plastic Ampule
491391 | NDC 63323-493-91 Unit of 5 | 1.5% (300 mg per 20 mL) (15 mg per mL) | NDC 63323-493-01 20 mL Plastic Ampule
491527 | NDC 63323-495-27 Unit of 25 | 2% (40 mg per 2 mL) (20 mg per mL) | NDC 63323-495-09 2 mL Single Dose Vial
491507 | NDC 63323-495-07 Unit of 25 | 2% (100 mg per 5 mL) (20 mg per mL) | NDC 63323-495-04 5 mL Single Dose Vial
491697 | NDC 63323-496-97 Unit of 5 | 2% (200 mg per 10 mL) (20 mg per mL) | NDC 63323-496-03 10 mL Plastic Ampule

Xylocaine® (lidocaine HCl and epinephrine Injection, USP) with Epinephrine 1:100,000

Product Code | Unit of Sale | Strength | Each
480217 | NDC 63323-482-17 Unit of 25 | 1% (100 mg per 10 mL) (10 mg per mL) | NDC 63323-482-01 10 mL Multiple Dose Vial
480227 | NDC 63323-482-27 Unit of 25 | 1% (200 mg per 20 mL) (10 mg per mL) | NDC 63323-482-03 20 mL Multiple Dose Vial
480257 | NDC 63323-482-57 Unit of 25 | 1% (500 mg per 50 mL) (10 mg per mL) | NDC 63323-482-05 50 mL Multiple Dose Vial
480327 | NDC 63323-483-27 Unit of 25 | 2% (400 mg per 20 mL) (20 mg per mL) | NDC 63323-483-03 20 mL Multiple Dose Vial
480357 | NDC 63323-483-57 Unit of 25 | 2% (1,000 mg per 50 mL) (20 mg per mL) | NDC 63323-483-01 50 mL Multiple Dose Vial

Xylocaine® (lidocaine HCl and epinephrine Injection, USP) with Epinephrine 1:200,000

Product Code | Unit of Sale | Strength | Each
480157 | NDC 63323-481-57; Unit of 25 | 0.5% (250 mg per 50 mL) (5 mg per mL) | NDC 63323-481-01 50 mL Multiple Dose Vial

Xylocaine®-MPF (lidocaine HCl and epinephrine Injection, USP) with Epinephrine 1:200,000

Product Code | Unit of Sale | Strength | Each
480717 | NDC 63323-487-17 Unit of 25 | 1% (100 mg per 10 mL) (10 mg per mL) | NDC 63323-487-01 10 mL Single Dose Vial
480737 | NDC 63323-487-37 Unit of 25 | 1% (300 mg per 30 mL) (10 mg per mL) | NDC 63323-487-07 30 mL Single Dose Vial
480731 | NDC 63323-487-31 Unit of 5 | 1% (300 mg per 30 mL) (10 mg per mL) | NDC 63323-487-03 30 mL Single Dose Vial
480817 | NDC 63323-488-17 Unit of 25 | 1.5% (150 mg per 10 mL) (15 mg per mL) | NDC 63323-488-01 10 mL Single Dose Vial
480837 | NDC 63323-488-37 Unit of 25 | 1.5% (450 mg per 30 mL) (15 mg per mL) | NDC 63323-488-07 30 mL Single Dose Vial
480831 | NDC 63323-488-31 Unit of 5 | 1.5% (450 mg per 30 mL) (15 mg per mL) | NDC 63323-488-03 30 mL Single Dose Vial
480917 | NDC 63323-489-17 Unit of 25 | 2% (200 mg per 10 mL) (20 mg per mL) | NDC 63323-489-01 10 mL Single Dose Vial
480927 | NDC 63323-489-27 Unit of 25 | 2% (400 mg per 20 mL) (20 mg per mL) | NDC 63323-489-02 20 mL Single Dose Vial
480921 | NDC 63323-489-21 Unit of 5 | 2% (400 mg per 20 mL) (20 mg per mL) | NDC 63323-489-03 20 mL Single Dose Vial

For single-dose vials and ampules: Discard unused portion.

All solutions should be stored at 20° to 25°C (68° to 77°F) [see USP Controlled Room Temperature].

Protect from light.

All trademarks are the property of Fresenius Kabi USA, LLC.

Fresenius Kabi Logo

www.fresenius-kabi.com

4 5 1 1 7 5 F

Revised: March 2019

MARCAINE - bupivacaine hydrochloride injection, solution

MARCAINE WITH EPINEPHRINE- bupivacaine hydrochloride and epinephrine bitartrate injection, solution

Hospira, Inc.

MarcaineTM
Bupivacaine Hydrochloride Injection, USP

MarcaineTM
With Epinephrine 1:200,000 (as bitartrate)
Bupivacaine Hydrochloride and Epinephrine Injection, USP

Rx only

DESCRIPTION

Bupivacaine hydrochloride is 2-Piperidinecarboxamide, 1-butyl-N-(2,6-dimethylphenyl)-,monohydrochloride, monohydrate, a white crystalline powder that is freely soluble in 95 percent ethanol, soluble in water, and slightly soluble in chloroform or acetone. It has the following structural formula:

Marcaine Structural Formula

Epinephrine is (-)-3,4-Dihydroxy-α-[(methylamino)methyl] benzyl alcohol. It has the following structural formula:

Epinephrine Structural Formula

MARCAINE is available in sterile isotonic solutions with and without epinephrine (as bitartrate) 1:200,000 for injection via local infiltration, peripheral nerve block, and caudal and lumbar epidural blocks. Solutions of MARCAINE may be autoclaved if they do not contain epinephrine. Solutions are clear and colorless.

Bupivacaine is related chemically and pharmacologically to the aminoacyl local anesthetics. It is a homologue of mepivacaine and is chemically related to lidocaine. All three of these anesthetics contain an amide linkage between the aromatic nucleus and the amino, or piperidine group. They differ in this respect from the procaine-type local anesthetics, which have an ester linkage.

MARCAINE—Sterile isotonic solutions containing sodium chloride. In multiple-dose vials, each mL also contains 1 mg methylparaben as antiseptic preservative. The pH of these solutions is adjusted to between 4 and 6.5 with sodium hydroxide or hydrochloric acid.

MARCAINE with epinephrine 1:200,000 (as bitartrate)—Sterile isotonic solutions containing sodium chloride. Each mL contains bupivacaine hydrochloride and 0.0091 mg epinephrine bitartrate, with 0.5 mg sodium metabisulfite, 0.001 mL monothioglycerol, and 2 mg ascorbic acid as antioxidants, 0.0017 mL 60% sodium lactate buffer, and 0.1 mg edetate calcium disodium as stabilizer. In multiple-dose vials, each mL also contains 1 mg methylparaben as antiseptic preservative. The pH of these solutions is adjusted to between 3.4 and 4.5 with sodium hydroxide or hydrochloric acid. The specific gravity of MARCAINE 0.5% with epinephrine 1:200,000 (as bitartrate) at 25°C is 1.008 and at 37°C is 1.008.

CLINICAL PHARMACOLOGY

Local anesthetics block the generation and the conduction of nerve impulses, presumably by increasing the threshold for electrical excitation in the nerve, by slowing the propagation of the nerve impulse, and by reducing the rate of rise of the action potential. In general, the progression of anesthesia is related to the diameter, myelination, and conduction velocity of affected nerve fibers. Clinically, the order of loss of nerve function is as follows: (1) pain, (2) temperature, (3) touch, (4) proprioception, and (5) skeletal muscle tone.

Systemic absorption of local anesthetics produces effects on the cardiovascular and central nervous systems (CNS). At blood concentrations achieved with normal therapeutic doses, changes in cardiac conduction, excitability, refractoriness, contractility, and peripheral vascular resistance are minimal. However, toxic blood concentrations depress cardiac conduction and excitability, which may lead to atrioventricular block, ventricular arrhythmias, and cardiac arrest, sometimes resulting in fatalities. In addition, myocardial contractility is depressed and peripheral vasodilation occurs, leading to decreased cardiac output and arterial blood pressure. Recent clinical reports and animal research suggest that these cardiovascular changes are more likely to occur after unintended
intravascular injection of bupivacaine. Therefore, incremental dosing is necessary.

Following systemic absorption, local anesthetics can produce CNS stimulation, depression, or both. Apparent central stimulation is manifested as restlessness, tremors and shivering progressing to convulsions, followed by depression and coma progressing ultimately to respiratory arrest. However,
the local anesthetics have a primary depressant effect on the medulla and on higher centers. The depressed stage may occur without a prior excited state.

Pharmacokinetics: The rate of systemic absorption of local anesthetics is dependent upon the total dose and concentration of drug administered, the route of administration, the vascularity of the administration site, and the presence or absence of epinephrine in the anesthetic solution. A dilute concentration of epinephrine (1:200,000 or 5 mcg/mL) usually reduces the rate of absorption and peak plasma concentration of MARCAINE, permitting the use of moderately larger total doses and sometimes prolonging the duration of action.

The onset of action with MARCAINE is rapid and anesthesia is long lasting. The duration of anesthesia is significantly longer with MARCAINE than with any other commonly used local anesthetic. It has also been noted that there is a period of analgesia that persists after the return of sensation, during which time the need for strong analgesics is reduced.

The onset of action following dental injections is usually 2 to 10 minutes and anesthesia may last two or three times longer than lidocaine and mepivacaine for dental use, in many patients up to 7 hours. The duration of anesthetic effect is prolonged by the addition of epinephrine 1:200,000.

Local anesthetics are bound to plasma proteins in varying degrees. Generally, the lower the plasma concentration of drug the higher the percentage of drug bound to plasma proteins.

Local anesthetics appear to cross the placenta by passive diffusion. The rate and degree of diffusion is governed by (1) the degree of plasma protein binding, (2) the degree of ionization, and (3) the degree of lipid solubility. Fetal/ maternal ratios of local anesthetics appear to be inversely related to the degree of
plasma protein binding, because only the free, unbound drug is available for placental transfer.

MARCAINE with a high protein binding capacity (95%) has a low fetal/maternal ratio (0.2 to 0.4). The extent of placental transfer is also determined by the degree of ionization and lipid solubility of the drug. Lipid soluble, nonionized drugs readily enter the fetal blood from the maternal circulation.

Depending upon the route of administration, local anesthetics are distributed to some extent to all body tissues, with high concentrations found in highly perfused organs such as the liver, lungs, heart, and brain.

Pharmacokinetic studies on the plasma profile of MARCAINE after direct intravenous injection suggest a three-compartment open model. The first compartment is represented by the rapid intravascular distribution of the drug. The second compartment represents the equilibration of the drug throughout
the highly perfused organs such as the brain, myocardium, lungs, kidneys, and liver. The third compartment represents an equilibration of the drug with poorly perfused tissues, such as muscle and fat. The elimination of drug from tissue distribution depends largely upon the ability of binding sites in the circulation to carry it to the liver where it is metabolized.

After injection of MARCAINE for caudal, epidural, or peripheral nerve block in man, peak levels of bupivacaine in the blood are reached in 30 to 45 minutes, followed by a decline to insignificant levels during the next three to six hours.

Various pharmacokinetic parameters of the local anesthetics can be significantly altered by the presence of hepatic or renal disease, addition of epinephrine, factors affecting urinary pH, renal blood flow, the route of drug administration, and the age of the patient. The half-life of MARCAINE in adults is 2.7 hours and in neonates 8.1 hours.

In clinical studies, elderly patients reached the maximal spread of analgesia and maximal motor blockade more rapidly than younger patients. Elderly patients also exhibited higher peak plasma concentrations following administration of this product. The total plasma clearance was decreased in these patients.

Amide-type local anesthetics such as MARCAINE are metabolized primarily in the liver via conjugation with glucuronic acid. Patients with hepatic disease, especially those with severe hepatic disease, may be more susceptible to the potential toxicities of the amide-type local anesthetics. Pipecoloxylidine is the major metabolite of MARCAINE.

The kidney is the main excretory organ for most local anesthetics and their metabolites. Urinary excretion is affected by urinary perfusion and factors affecting urinary pH. Only 6% of bupivacaine is excreted unchanged in the urine.

When administered in recommended doses and concentrations, MARCAINE does not ordinarily produce irritation or tissue damage.

INDICATIONS AND USAGE

MARCAINE is indicated for the production of local or regional anesthesia or analgesia for surgery, dental and oral surgery procedures, diagnostic and therapeutic procedures, and for obstetrical procedures. Only the 0.25% and 0.5% concentrations are indicated for obstetrical anesthesia. (See WARNINGS.)

Experience with nonobstetrical surgical procedures in pregnant patients is not sufficient to recommend use of 0.75% concentration of MARCAINE in these patients.

MARCAINE is not recommended for intravenous regional anesthesia (Bier Block). See WARNINGS.

The routes of administration and indicated MARCAINE concentrations are:

- local infiltration | 0.25%
- peripheral nerve block | 0.25% and 0.5%
- retrobulbar block | 0.75%
- sympathetic block | 0.25%
- lumbar epidural | 0.25%, 0.5%, and 0.75%; (0.75% not for obstetrical anesthesia)
- caudal | 0.25% and 0.5%
- epidural test dose | 0.5% with epinephrine 1:200,000
- dental blocks | 0.5% with epinephrine 1:200,000

(See DOSAGE AND ADMINISTRATION for additional information).

Standard textbooks should be consulted to determine the accepted procedures and techniques for the administration of MARCAINE.

CONTRAINDICATIONS

MARCAINE is contraindicated in obstetrical paracervical block anesthesia. Its use in this technique has resulted in fetal bradycardia and death.

MARCAINE is contraindicated in patients with a known hypersensitivity to it or to any local anesthetic agent of the amide-type or to other components of MARCAINE solutions.

WARNINGS

THE 0.75% CONCENTRATION OF MARCAINE IS NOT RECOMMENDED FOR OBSTETRICAL ANESTHESIA. THERE HAVE BEEN REPORTS OF CARDIAC ARREST WITH DIFFICULT RESUSCITATION OR DEATH DURING USE OF MARCAINE FOR EPIDURAL ANESTHESIA IN OBSTETRICAL PATIENTS. IN MOST CASES, THIS HAS FOLLOWED USE OF THE 0.75% CONCENTRATION. RESUSCITATION HAS BEEN DIFFICULT OR IMPOSSIBLE DESPITE APPARENTLY ADEQUATE PREPARATION AND APPROPRIATE MANAGEMENT. CARDIAC ARREST HAS OCCURRED AFTER CONVULSIONS RESULTING FROM SYSTEMIC TOXICITY, PRESUMABLY FOLLOWING UNINTENTIONAL INTRAVASCULAR INJECTION. THE 0.75% CONCENTRATION SHOULD BE RESERVED FOR SURGICAL PROCEDURES WHERE A HIGH DEGREE OF MUSCLE RELAXATION AND PROLONGED EFFECT ARE NECESSARY.

LOCAL ANESTHETICS SHOULD ONLY BE EMPLOYED BY CLINICIANS WHO ARE WELL VERSED IN DIAGNOSIS AND MANAGEMENT OF DOSE-RELATED TOXICITY AND OTHER ACUTE EMERGENCIES WHICH MIGHT ARISE FROM THE BLOCK TO BE EMPLOYED, AND THEN ONLY AFTER INSURING THE IMMEDIATE AVAILABILITY OF OXYGEN, OTHER RESUSCITATIVE DRUGS, CARDIOPULMONARY RESUSCITATIVE EQUIPMENT, AND THE PERSONNEL RESOURCES NEEDED FOR PROPER MANAGEMENT OF TOXIC REACTIONS AND RELATED EMERGENCIES. (See also ADVERSE REACTIONS, PRECAUTIONS, and OVERDOSAGE.) DELAY IN PROPER MANAGEMENT OF DOSE-RELATED TOXICITY, UNDERVENTILATION FROM ANY CAUSE, AND/OR ALTERED SENSITIVITY MAY LEAD TO THE DEVELOPMENT OF ACIDOSIS, CARDIAC ARREST AND, POSSIBLY, DEATH.

Methemoglobinemia: Cases of methemoglobinemia have been reported in association with local anesthetic use. Although all patients are at risk for methemoglobinemia, patients with glucose-6-phosphate dehydrogenase deficiency, congenital or idiopathic methemoglobinemia, cardiac or pulmonary compromise, infants under 6 months of age, and concurrent exposure to oxidizing agents or their metabolites are more susceptible to developing clinical manifestations of the condition. If local anesthetics must be used in these patients, close monitoring for symptoms and signs of methemoglobinemia is recommended.

Signs of methemoglobinemia may occur immediately or may be delayed some hours after exposure, and are characterized by a cyanotic skin discoloration and/or abnormal coloration of the blood. Methemoglobin levels may continue to rise; therefore, immediate treatment is required to avert more serious CNS and cardiovascular adverse effects, including seizures, coma, arrhythmias, and death. Discontinue MARCAINE and any other oxidizing agents. Depending on the severity of the signs and symptoms, patients may respond to supportive care, i.e., oxygen therapy, hydration. A more severe clinical presentation may require treatment with methylene blue, exchange transfusion, or hyperbaric oxygen.

Local anesthetic solutions containing antimicrobial preservatives, i.e., those supplied in multiple-dose vials, should not be used for epidural or caudal anesthesia because safety has not been established with regard to intrathecal injection, either intentionally or unintentionally, of such preservatives.

Intra-articular infusions of local anesthetics following arthroscopic and other surgical procedures is an unapproved use, and there have been post-marketing reports of chondrolysis in patients receiving such infusions. The majority of reported cases of chondrolysis have involved the shoulder joint; cases of gleno-humeral chondrolysis have been described in pediatric and adult patients following intra-articular infusions of local anesthetics with and without epinephrine for periods of 48 to 72 hours. There is insufficient information to determine whether shorter infusion periods are not associated with these findings. The time of onset of symptoms, such as joint pain, stiffness and loss of motion can be variable, but may begin as early as the 2nd month after surgery. Currently, there is no effective treatment for chondrolysis; patients who experienced chondrolysis have required additional diagnostic and therapeutic procedures and some required arthroplasty or shoulder replacement.

It is essential that aspiration for blood or cerebrospinal fluid (where applicable) be done prior to injecting any local anesthetic, both the original dose and all subsequent doses, to avoid intravascular or subarachnoid injection. However, a negative aspiration does not ensure against an intravascular or subarachnoid injection.

MARCAINE with epinephrine 1:200,000 or other vasopressors should not be used concomitantly with ergot-type oxytocic drugs, because a severe persistent hypertension may occur. Likewise, solutions of MARCAINE containing a vasoconstrictor, such as epinephrine, should be used with extreme caution in patients receiving monoamineoxidase inhibitors (MAOI) or antidepressants of the triptyline or imipramine types, because severe prolonged hypertension may result.

Until further experience is gained in pediatric patients younger than 12 years, administration of MARCAINE in this age group is not recommended.

Mixing or the prior or intercurrent use of any other local anesthetic with MARCAINE cannot be recommended because of insufficient data on the clinical use of such mixtures.

There have been reports of cardiac arrest and death during the use of MARCAINE for intravenous regional anesthesia (Bier Block). Information on safe dosages and techniques of administration of MARCAINE in this procedure is lacking. Therefore, MARCAINE is not recommended for use in this technique.

MARCAINE with epinephrine 1:200,000 contains sodium metabisulfite, a sulfite that may cause allergic- type reactions including anaphylactic symptoms and life-threatening or less severe asthmatic episodes in certain susceptible people. The overall prevalence of sulfite sensitivity in the general population is unknown and probably low. Sulfite sensitivity is seen more frequently in asthmatic than in nonasthmatic people. Single-dose ampuls and single-dose vials of MARCAINE without epinephrine do not contain sodium metabisulfite.

PRECAUTIONS

General: The safety and effectiveness of local anesthetics depend on proper dosage, correct technique, adequate precautions, and readiness for emergencies. Resuscitative equipment, oxygen, and other resuscitative drugs should be available for immediate use (See WARNINGS, ADVERSE REACTIONS, and OVERDOSAGE). During major regional nerve blocks, the patient should have intravenous fluids running via an indwelling catheter to assure a functioning intravenous pathway. The lowest dosage of local anesthetic that results in effective anesthesia should be used to avoid high plasma levels and serious adverse effects. The rapid injection of a large volume of local anesthetic solution should be avoided and fractional (incremental) doses should be used when feasible.

Epidural Anesthesia: During epidural administration of MARCAINE, 0.5% and 0.75% solutions should be administered in incremental doses of 3 mL to 5 mL with sufficient time between doses to detect toxic manifestations of unintentional intravascular or intrathecal injection. Injections should be made slowly, with frequent aspirations before and during the injection to avoid intravascular injection. Syringe aspirations should also be performed before and during each
supplemental injection in continuous (intermittent) catheter techniques. An intravascular injection is still possible even if aspirations for blood are negative.

During the administration of epidural anesthesia, it is recommended that a test dose be administered initially and the effects monitored before the full dose is given. When using a "continuous" catheter technique, test doses should be given prior to both the original and all reinforcing doses, because plastic tubing in the epidural space can migrate into a blood vessel or through the dura. When clinical conditions permit, the test dose should contain epinephrine (10 mcg to 15 mcg has been suggested) to serve as a warning of unintended intravascular injection. If injected into a blood vessel, this amount of epinephrine is likely to produce a transient "epinephrine response" within 45 seconds, consisting of an increase in heart rate and/or systolic blood pressure, circumoral pallor, palpitations, and nervousness in the unsedated patient. The sedated patient may exhibit only a pulse rate increase of 20 or more beats per minute for 15 or more seconds. Therefore, following the test dose, the heart rate should be monitored for a heart rate increase. Patients on beta-blockers may not manifest changes in heart rate, but blood pressure monitoring can detect a transient rise in systolic blood pressure. The test dose should also contain 10 mg to 15
mg of MARCAINE or an equivalent amount of another local anesthetic to detect an unintended intrathecal administration. This will be evidenced within a few minutes by signs of spinal block (e.g., decreased sensation of the buttocks, paresis of the legs, or, in the sedated patient, absent knee jerk). The Test Dose formulation of MARCAINE contains 15 mg of bupivacaine and 15 mcg of epinephrine in a volume of 3 mL. An intravascular or subarachnoid injection is still possible even if results of the test dose are negative. The test dose itself may produce a systemic toxic reaction, high spinal or epinephrine-induced cardiovascular effects.

Injection of repeated doses of local anesthetics may cause significant increases in plasma levels with each repeated dose due to slow accumulation of the drug or its metabolites, or to slow metabolic degradation. Tolerance to elevated blood levels varies with the status of the patient. Debilitated, elderly patients and acutely ill patients should be given reduced doses commensurate with their age and physical status. Local anesthetics should also be used with caution in patients with hypotension or heartblock.

Careful and constant monitoring of cardiovascular and respiratory (adequacy of ventilation) vital signs and the patient's state of consciousness should be performed after each local anesthetic injection. It should be kept in mind at such times that restlessness, anxiety, incoherent speech, lightheadedness, numbness and tingling of the mouth and lips, metallic taste, tinnitus, dizziness, blurred vision, tremors, twitching, depression, or drowsiness may be early warning signs of CNS toxicity.

Local anesthetic solutions containing a vasoconstrictor should be used cautiously and in carefully restricted quantities in areas of the body supplied by end arteries or having otherwise compromised blood supply such as digits, nose, external ear, or penis. Patients with hypertensive vascular disease may exhibit exaggerated vasoconstrictor response. Ischemic injury or necrosis may result.

Because amide-local anesthetics such as MARCAINE are metabolized by the liver, these drugs, especially repeat doses, should be used cautiously in patients with hepatic disease. Patients with severe hepatic disease, because of their inability to metabolize local anesthetics normally, are at a greater risk of developing toxic plasma concentrations. Local anesthetics should also be used with caution in patients with impaired cardiovascular function because they may be less able to compensate for functional changes associated with the prolongation of AV conduction produced by these drugs.

Serious dose-related cardiac arrhythmias may occur if preparations containing a vasoconstrictor such as epinephrine are employed in patients during or following the administration of potent inhalation anesthetics. In deciding whether to use these products concurrently in the same patient, the combined action of both agents upon the myocardium, the concentration and volume of vasoconstrictor used, and the time since injection, when applicable, should be taken into account.

Many drugs used during the conduct of anesthesia are considered potential triggering agents for familial malignant hyperthermia. Because it is not known whether amide-type local anesthetics may trigger this reaction and because the need for supplemental general anesthesia cannot be predicted in advance, it is suggested that a standard protocol for management should be available. Early unexplained signs of tachycardia, tachypnea, labile blood pressure, and metabolic acidosis may precede temperature elevation. Successful outcome is dependent on early diagnosis, prompt discontinuance of the suspect triggering agent(s) and prompt institution of treatment, including oxygen therapy, indicated supportive measures and dantrolene (Consult dantrolene sodium intravenous package insert before using).

Use in Head and Neck Area: Small doses of local anesthetics injected into the head and neck area, including retrobulbar, dental, and stellate ganglion blocks, may produce adverse reactions similar to systemic toxicity seen with unintentional intravascular injections of larger doses. The injection procedures require the utmost care. Confusion, convulsions, respiratory depression, and/or respiratory arrest, and cardiovascular stimulation or depression have been reported. These reactions may be due to intra-arterial injection of the local anesthetic with retrograde flow to the cerebral circulation. They may also be due to puncture of the dural sheath of the optic nerve during retrobulbar block with diffusion of any local anesthetic along the subdural space to the midbrain. Patients receiving these blocks should have their circulation and respiration monitored and be constantly observed. Resuscitative equipment and personnel for treating adverse reactions should be immediately available. Dosage recommendations should not be exceeded (See DOSAGE AND ADMINISTRATION).

Use in Ophthalmic Surgery: Clinicians who perform retrobulbar blocks should be aware that there have been reports of respiratory arrest following local anesthetic injection. Prior to retrobulbar block, as with all other regional procedures, the immediate availability of equipment, drugs, and personnel to manage respiratory arrest or depression, convulsions, and cardiac stimulation or depression should be assured (see also WARNINGS and Use In Head and Neck Area, above). As with other anesthetic procedures, patients should be constantly monitored following ophthalmic blocks or signs of these adverse reactions, which may occur following relatively low total doses.

A concentration of 0.75% bupivacaine is indicated for retrobulbar block; however, this concentration is not indicated for any other peripheral nerve block, including the facial nerve, and not indicated for local infiltration, including the conjunctiva (see INDICATIONS AND USAGE and PRECAUTIONS, General). Mixing MARCAINE with other local anesthetics is not recommended because of insufficient data on the clinical use of such mixtures.

When MARCAINE 0.75% is used for retrobulbar block, complete corneal anesthesia usually precedes onset of clinically acceptable external ocular muscle akinesia. Therefore, presence of akinesia rather than anesthesia alone should determine readiness of the patient for surgery.

Use in Dentistry: Because of the long duration of anesthesia, when MARCAINE 0.5% with epinephrine is used for dental injections, patients should be cautioned about the possibility of inadvertent trauma to tongue, lips, and buccal mucosa and advised not to chew solid foods or test the anesthetized area by biting or probing.

Information for Patients: When appropriate, patients should be informed in advance that they may experience temporary loss of sensation and motor activity, usually in the lower half of the body, following proper administration of caudal or epidural anesthesia. Also, when appropriate, the physician should discuss other information including adverse reactions in the package insert of MARCAINE.

Patients receiving dental injections of MARCAINE should be cautioned not to chew solid foods or test the anesthetized area by biting or probing until anesthesia has worn off (up to 7 hours).

Inform patients that use of local anesthetics may cause methemoglobinemia, a serious condition that must be treated promptly. Advise patients or caregivers to seek immediate medical attention if they or someone in their care experience the following signs or symptoms: pale, gray, or blue colored skin (cyanosis); headache; rapid heart rate; shortness of breath; lightheadedness; or fatigue.

Clinically Significant Drug Interactions: The administration of local anesthetic solutions containing epinephrine or norepinephrine to patients receiving monoamine oxidase inhibitors or tricyclic antidepressants may produce severe, prolonged hypertension. Concurrent use of these agents should generally be avoided. In situations when concurrent therapy is necessary, careful patient monitoring is essential.

Concurrent administration of vasopressor drugs and of ergot-type oxytocic drugs may cause severe, persistent hypertension or cerebrovascular accidents.

Phenothiazines and butyrophenones may reduce or reverse the pressor effect of epinephrine.

Patients who are administered local anesthetics are at increased risk of developing methemoglobinemia when concurrently exposed to following drugs, which could include other local anesthetics:

Examples of Drugs Associated with Methemoglobinemia:

Class | Examples
Nitrates/Nitrites | nitric oxide, nitroglycerin, nitroprusside, nitrous oxide
Local anesthetics | articaine, benzocaine, bupivacaine, lidocaine, mepivacaine, prilocaine, procaine, ropivacaine, tetracaine
Antine plastic agents | cyclophosphamide, flu amide, hydroxyurea, isofamide, rasburicase
Antibiotics | dapsone, nitrofurantoin, para-aminosalicylic acid, sulfonamides
Antimalarials | chloroquine, primaquine
Anticonvulsants | phenobarbital, phenytoin, sodium valproate
Other drugs | acetaminophen, metoclopramide, quinine, sulfasalazine

Carcinogenesis, Mutagenesis, Impairment of Fertility: Long-term studies in animals to evaluate the carcinogenic potential of bupivacaine hydrochloride have not been conducted. The mutagenic potential and the effect on fertility of bupivacaine hydrochloride have not been determined.

Pregnancy: There are no adequate and well-controlled studies in pregnant women. MARCAINE should be used during pregnancy only if the potential benefit justifies the potential risk to the fetus. Bupivacaine hydrochloride produced developmental toxicity when administered subcutaneously to pregnant rats and rabbits at clinically relevant doses. This does not exclude the use of MARCAINE at term for obstetrical anesthesia or analgesia (See Labor and Delivery).

Bupivacaine hydrochloride was administered subcutaneously to rats at doses of 4.4, 13.3, & 40 mg/kg and to rabbits at doses of 1.3, 5.8, & 22.2 mg/kg during the period of organogenesis (implantation to closure of the hard palate). The high doses are comparable to the daily maximum recommended
human dose (MRHD) of 400 mg/day on a mg/m^2 body surface area (BSA) basis. No embryo-fetal effects were observed in rats at the high dose which caused increased maternal lethality. An increase in embryo-fetal deaths was observed in rabbits at the high dose in the absence of maternal toxicity with the fetal No Observed Adverse Effect Level representing approximately 1/5th the MRHD on a BSA basis.

In a rat pre- and post-natal development study (dosing from implantation through weaning) conducted at subcutaneous doses of 4.4, 13.3, & 40 mg/kg, decreased pup survival was observed at the high dose. The high dose is comparable to the daily MRHD of 400 mg/day on a BSA basis.

Labor and Delivery: SEE BOXED WARNING REGARDING OBSTETRICAL USE OF 0.75% MARCAINE.

MARCAINE is contraindicated for obstetrical paracervical block anesthesia.

Local anesthetics rapidly cross the placenta, and when used for epidural, caudal, or pudendal block anesthesia, can cause varying degrees of maternal, fetal, and neonatal toxicity (See CLINICAL PHARMACOLOGY, Pharmacokinetics). The incidence and degree of toxicity depend upon the procedure performed, the type, and amount of drug used, and the technique of drug administration. Adverse reactions in the parturient, fetus, and neonate involve alterations of the CNS, peripheral vascular tone, and cardiac function.

Maternal hypotension has resulted from regional anesthesia. Local anesthetics produce vasodilation by blocking sympathetic nerves. Elevating the patient's legs and positioning her on her left side will help prevent decreases in blood pressure. The fetal heart rate also should be monitored continuously and electronic fetal monitoring is highly advisable.

Epidural, caudal, or pudendal anesthesia may alter the forces of parturition through changes in uterine contractility or maternal expulsive efforts. Epidural anesthesia has been reported to prolong the second stage of labor by removing the parturient's reflex urge to bear down or by interfering with motor function. The use of obstetrical anesthesia may increase the need for forceps assistance.

The use of some local anesthetic drug products during labor and delivery may be followed by diminished muscle strength and tone for the first day or two of life. This has not been reported with bupivacaine.

It is extremely important to avoid aortocaval compression by the gravid uterus during administration of regional block to parturients. To do this, the patient must be maintained in the left lateral decubitus position or a blanket roll or sandbag may be placed beneath the right hip and gravid uterus displaced to
the left.
Nursing Mothers: Bupivacaine has been reported to be excreted in human milk suggesting that the nursing infant could be theoretically exposed to a dose of the drug. Because of the potential for serious adverse reactions in nursing infants from bupivacaine, a decision should be made whether to discontinue nursing or not administer bupivacaine, taking into account the importance of the drug to the mother.

Pediatric Use: Until further experience is gained in pediatric patients younger than 12 years, administration of MARCAINE in this age group is not recommended. Continuous infusions of bupivacaine in children have been reported to result in high systemic levels of bupivacaine and seizures; high plasma levels may also be associated with cardiovascular abnormalities (See WARNINGS, PRECAUTIONS, and OVERDOSAGE).

Geriatric Use: Patients over 65 years, particularly those with hypertension, may be at increased risk for developing hypotension while undergoing anesthesia with MARCAINE (See ADVERSE REACTIONS).

Elderly patients may require lower doses of MARCAINE (See PRECAUTIONS, Epidural Anesthesia and DOSAGE AND ADMINISTRATION).

In clinical studies, differences in various pharmacokinetic parameters have been observed between elderly and younger patients (See CLINICAL PHARMACOLOGY).

This product is known to be substantially excreted by the kidney, and the risk of toxic reactions to this drug may be greater in patients with impaired renal function. Because elderly patients are more likely to have decreased renal function, care should be taken in dose selection, and it may be useful to
monitor renal function (See CLINICAL PHARMACOLOGY).

ADVERSE REACTIONS

Reactions to MARCAINE are characteristic of those associated with other amide-type local anesthetics. A major cause of adverse reactions to this group of drugs is excessive plasma levels, which may be due to overdosage, unintentional intravascular injection, or slow metabolic degradation.

The most commonly encountered acute adverse experiences which demand immediate counter-measures are related to the CNS and the cardiovascular system. These adverse experiences are generally dose related and due to high plasma levels which may result from overdosage, rapid absorption from the
injection site, diminished tolerance, or from unintentional intravascular injection of the local anesthetic solution. In addition to systemic dose-related toxicity, unintentional subarachnoid injection of drug during the intended performance of caudal or lumbar epidural block or nerve blocks near the vertebral column (especially in the head and neck region) may result in underventilation or apnea ("Total or High Spinal"). Also, hypotension due to loss of sympathetic tone and respiratory paralysis or underventilation due to cephalad extension of the motor level of anesthesia may occur. This may lead to secondary cardiac arrest if untreated. Patients over 65 years, particularly those with hypertension, may be at increased risk for experiencing the hypotensive effects of MARCAINE. Factors influencing plasma protein binding, such as acidosis, systemic diseases which alter protein production, or competition of other drugs for protein binding sites, may diminish individual tolerance.

CNS Reactions: These are characterized by excitation and/or depression. Restlessness, anxiety, dizziness, tinnitus, blurred vision, or tremors may occur, possibly proceeding to convulsions. However, excitement may be transient or absent, with depression being the first manifestation of an adverse reaction. This may quickly be followed by drowsiness merging into unconsciousness and respiratory arrest. Other CNS effects may be nausea, vomiting, chills, and constriction of the pupils.

The incidence of convulsions associated with the use of local anesthetics varies with the procedure used and the total dose administered. In a survey of studies of epidural anesthesia, overt toxicity progressing to convulsions occurred in approximately 0.1% of local anesthetic administrations.

Cardiovascular System Reactions: High doses or unintentional intravascular injection may lead to high plasma levels and related depression of the myocardium, decreased cardiac output, heartblock, hypotension, bradycardia, ventricular arrhythmias, including ventricular tachycardia and ventricular fibrillation, and cardiac arrest (See WARNINGS, PRECAUTIONS, and OVERDOSAGE).

Allergic: Allergic-type reactions are rare and may occur as a result of sensitivity to the local anesthetic or to other formulation ingredients, such as the antimicrobial preservative methylparaben contained in multiple-dose vials or sulfites in epinephrine-containing solutions. These reactions are
characterized by signs such as urticaria, pruritus, erythema, angioneurotic edema (including laryngeal edema), tachycardia, sneezing, nausea, vomiting, dizziness, syncope, excessive sweating, elevated temperature, and possibly, anaphylactoid-like symptomatology (including severe hypotension). Cross sensitivity among members of the amide-type local anesthetic group has been reported. The usefulness of screening for sensitivity has not been definitely established.

Neurologic: The incidences of adverse neurologic reactions associated with the use of local anesthetics may be related to the total dose of local anesthetic administered and are also dependent upon the particular drug used, the route of administration, and the physical status of the patient. Many of these
effects may be related to local anesthetic techniques, with or without a contribution from the drug.

In the practice of caudal or lumbar epidural block, occasional unintentional penetration of the subarachnoid space by the catheter or needle may occur. Subsequent adverse effects may depend partially on the amount of drug administered intrathecally and the physiological and physical effects of a dural puncture. A high spinal is characterized by paralysis of the legs, loss of consciousness, respiratory paralysis, and bradycardia.

Neurologic effects following epidural or caudal anesthesia may include spinal block of varying magnitude (including high or total spinal block); hypotension secondary to spinal block; urinary retention; fecal and urinary incontinence; loss of perineal sensation and sexual function; persistent anesthesia, paresthesia, weakness, paralysis of the lower extremities and loss of sphincter control all of which may have slow, incomplete, or no recovery; headache; backache; septic meningitis; meningismus; slowing of labor; increased incidence of forceps delivery; and cranial nerve palsies due to traction on nerves from loss of cerebrospinal fluid.

Neurologic effects following other procedures or routes of administration may include persistent anesthesia, paresthesia, weakness, paralysis, all of which may have slow, incomplete, or no recovery.

OVERDOSAGE

Acute emergencies from local anesthetics are generally related to high plasma levels encountered during therapeutic use of local anesthetics or to unintended subarachnoid injection of local anesthetic solution (See ADVERSE REACTIONS, WARNINGS, and PRECAUTIONS).

Management of Local Anesthetic Emergencies: The first consideration is prevention, best accomplished by careful and constant monitoring of cardiovascular and respiratory vital signs and the patient's state of consciousness after each local anesthetic injection. At the first sign of change, oxygen should be administered.

The first step in the management of systemic toxic reactions, as well as underventilation or apnea due to unintentional subarachnoid injection of drug solution, consists of immediate attention to the establishment and maintenance of a patent airway and effective assisted or controlled ventilation with 100% oxygen with a delivery system capable of permitting immediate positive airway pressure by mask. This may prevent convulsions if they have not already occurred.

If necessary, use drugs to control the convulsions. A 50 mg to 100 mg bolus intravenous injection of succinylcholine will paralyze the patient without depressing the CNS or cardiovascular systems and facilitate ventilation. A bolus intravenous dose of 5 mg to 10 mg of diazepam or 50 mg to 100 mg of thiopental will permit ventilation and counteract CNS stimulation, but these drugs also depress CNS, respiratory, and cardiac function, add to postictal depression and may result in apnea. Intravenous barbiturates, anticonvulsant agents, or muscle relaxants should only be administered by those familiar with their use. Immediately after the institution of these ventilatory measures, the adequacy of the circulation should be evaluated. Supportive treatment of circulatory depression may require administration of intravenous fluids, and when appropriate, a vasopressor dictated by the clinical situation (such as ephedrine or epinephrine to enhance myocardial contractile force).

Endotracheal intubation, employing drugs and techniques familiar to the clinician, may be indicated after initial administration of oxygen by mask if difficulty is encountered in the maintenance of a patent airway, or if prolonged ventilatory support (assisted or controlled) is indicated.

Recent clinical data from patients experiencing local anesthetic-induced convulsions demonstrated rapid development of hypoxia, hypercarbia, and acidosis with bupivacaine within a minute of the onset of convulsions. These observations suggest that oxygen consumption and carbon dioxide production are greatly increased during local anesthetic convulsions and emphasize the importance of immediate and effective ventilation with oxygen which may avoid cardiac arrest.

If not treated immediately, convulsions with simultaneous hypoxia, hypercarbia, and acidosis plus myocardial depression from the direct effects of the local anesthetic may result in cardiac arrhythmias, bradycardia, asystole, ventricular fibrillation, or cardiac arrest. Respiratory abnormalities, including apnea, may occur. Underventilation or apnea due to unintentional subarachnoid injection of local anesthetic solution may produce these same signs and also lead to
cardiac arrest if ventilatory support is not instituted. If cardiac arrest should occur, successful outcome may require prolonged resuscitative efforts.

The supine position is dangerous in pregnant women at term because of aortocaval compression by the gravid uterus. Therefore during treatment of systemic toxicity, maternal hypotension or fetal bradycardia following regional block, the parturient should be maintained in the left lateral decubitus position if possible, or manual displacement of the uterus off the great vessels be accomplished. The mean seizure dosage of bupivacaine in rhesus monkeys was found to be 4.4 mg/kg with mean arterial plasma concentration of 4.5 mcg/mL. The intravenous and subcutaneous LD50 in mice is 6 mg/kg to 8 mg/kg and 38 mg/kg to 54 mg/kg respectively.

DOSAGE AND ADMINISTRATION

The dose of any local anesthetic administered varies with the anesthetic procedure, the area to be anesthetized, the vascularity of the tissues, the number of neuronal segments to be blocked, the depth of anesthesia and degree of muscle relaxation required, the duration of anesthesia desired, individual tolerance, and the physical condition of the patient. The smallest dose and concentration required to produce the desired result should be administered. Dosages of MARCAINE should be reduced for elderly and/or debilitated patients and patients with cardiac and/or liver disease. The rapid injection of a large volume of local anesthetic solution should be avoided and fractional (incremental) doses should be used when feasible.

For specific techniques and procedures, refer to standard textbooks.

There have been adverse event reports of chondrolysis in patients receiving intra-articular infusions of local anesthetics following arthroscopic and other surgical procedures. MARCAINE is not approved for this use (see WARNINGS and DOSAGE AND ADMINISTRATION).

In recommended doses, MARCAINE produces complete sensory block, but the effect on motor function differs among the three concentrations.

0.25%—when used for caudal, epidural, or peripheral nerve block, produces incomplete motor block. Should be used for operations in which muscle relaxation is not important, or when another means of providing muscle relaxation is used concurrently. Onset of action may be slower than with the 0.5%
or 0.75% solutions.

0.5%— provides motor blockade for caudal, epidural, or nerve block, but muscle relaxation may be inadequate for operations in which complete muscle relaxation is essential.

0.75%—produces complete motor block. Most useful for epidural block in abdominal operations requiring complete muscle relaxation, and for retrobulbar anesthesia. Not for obstetrical anesthesia.

The duration of anesthesia with MARCAINE is such that for most indications, a single-dose is sufficient.
Maximum dosage limit must be individualized in each case after evaluating the size and physical status of the patient, as well as the usual rate of systemic absorption from a particular injection site. Most experience to date is with single-doses of MARCAINE up to 225 mg with epinephrine 1:200,000 and 175 mg without epinephrine; more or less drug may be used depending on individualization of each case.
These doses may be repeated up to once every three hours. In clinical studies to date, total daily doses have been up to 400 mg. Until further experience is gained, this dose should not be exceeded in 24 hours. The duration of anesthetic effect may be prolonged by the addition of epinephrine.

The dosages in Table 1 have generally proved satisfactory and are recommended as a guide for use in the average adult. These dosages should be reduced for elderly or debilitated patients. Until further experience is gained, MARCAINE is not recommended for pediatric patients younger than 12 years.
MARCAINE is contraindicated for obstetrical paracervical blocks, and is not recommended for intravenous regional anesthesia (Bier Block).

Use in Epidural Anesthesia: During epidural administration of MARCAINE, 0.5% and 0.75% solutions should be administered in incremental doses of 3 mL to 5 mL with sufficient time between doses to detect toxic manifestations of unintentional intravascular or intrathecal injection. In obstetrics, only the 0.5% and 0.25% concentrations should be used; incremental doses of 3 mL to 5 mL of the 0.5% solution not exceeding 50 mg to 100 mg at any dosing interval are recommended. Repeat doses should be preceded by a test dose containing epinephrine if not contraindicated. Use only the single-dose ampuls and single-dose vials for caudal or epidural anesthesia; the multiple-dose vials contain a preservative and therefore should not be used for these procedures.

Test Dose for Caudal and Lumbar Epidural Blocks: The Test Dose of MARCAINE (0.5% bupivacaine with 1:200,000 epinephrine in a 3 mL ampul) is recommended for use as a test dose when clinical conditions permit prior to caudal and lumbar epidural blocks. This may serve as a warning of unintended intravascular or subarachnoid injection (See PRECAUTIONS). The pulse rate and other signs should be monitored carefully immediately following each test dose administration to detect possible intravascular injection, and adequate time for onset of spinal block should be allotted to detect possible intrathecal injection. An intravascular or subarachnoid injection is still possible even if results of the test dose are negative. The test dose itself may produce a systemic toxic reaction, high spinal or cardiovascular effects from the epinephrine (See WARNINGS and OVERDOSAGE).

Use in Dentistry: The 0.5% concentration with epinephrine is recommended for infiltration and block injection in the maxillary and mandibular area when a longer duration of local anesthetic action is desired, such as for oral surgical procedures generally associated with significant postoperative pain. The average dose of 1.8 mL (9 mg) per injection site will usually suffice; an occasional second dose of 1.8 mL (9 mg) may be used if necessary to produce adequate anesthesia after making allowance for 2 to 10 minutes onset time (See CLINICAL PHARMACOLOGY). The lowest effective dose should be employed and time should be allowed between injections; it is recommended that the total dose for all injection sites, spread out over a single dental sitting, should not ordinarily exceed 90 mg for a healthy adult patient (ten 1.8 mL injections of 0.5% MARCAINE with epinephrine). Injections should be made slowly and with frequent aspirations. Until further experience is gained, MARCAINE in dentistry is not recommended for pediatric patients younger than 12 years.

Unused portions of solution not containing preservatives, i.e., those supplied in single-dose ampuls and single-dose vials, should be discarded following initial use.

This product should be inspected visually for particulate matter and discoloration prior to administration whenever solution and container permit. Solutions which are discolored or which contain particulate matter should not be administered.

Table 1. Recommended Concentrations and Doses of MARCAINE

Type of Block | Conc. | Each Dose |  | Motor Block^1
Type of Block | Conc. | (mL) | (mg) | Motor Block^1
Local Infiltration | 0.25%^4 | up to max. | up to max. | -------
Epidural | 0.75%^2,4 | 10-20 | 75-150 | complete
 | 0.5%^4 | 10-20 | 50-100 | moderate to complete
 | 0.25%^4 | 10-20 | 25-50 | partial to moderate
Caudal | 0.5%^4 | 15-30 | 75-150 | moderate to complete
 | 0.25%^4 | 15-30 | 37.5-75 | moderate
Peripheral nerves | 0.5%^4 | 5 to max. | 25 to max. | moderate to complete
 | 0.25%^4 | 5 to max. | 12.5 to max. | moderate to complete
Retrobulbar# | 0.75%^4 | 2 to 4 | 15 to 30 | complete
Sympathetic Dental^3 | 0.25% | 20-50 | 50-125 | -------
 | 0.5% w/epi | 1.8-3.6 per site | 9-18 per site | -------
Epidural^3 | 0.5% | 2-3 | 10-15 | -------
Test Dose | w/epi |  | (10-15 micrograms epinephrine)

^1 With continuous (intermittent) techniques, repeat doses increase the degree of motor block. The first repeat dose of 0.5% may produce complete motor block. Intercostal nerve block with 0.25% may also produce complete motor block for intra-abdominal surgery.

^2 For single-dose use, not for intermittent epidural technique. Not for obstetrical anesthesia.

^3 See PRECAUTIONS.

^4 Solutions with or without epinephrine.

HOW SUPPLIED

These solutions are not for spinal anesthesia.

Store at 20 to 25°C (68 to 77°F); excursions permitted between 15° to 30°C (59° to 86°F). [See USP Controlled Room Temperature.]

MARCAINE―Solutions of MARCAINE that do not contain epinephrine may be autoclaved. Autoclave at 15-pound pressure, 121°C (250°F) for 15 minutes.

Unit of Sale | Concentration | Each
0.25% Contains 2.5 mg bupivacaine hydrochloride per mL.
NDC 0409-1559-10 Tray of 10 | 25 mg/10 mL (2.5 mg/mL) | NDC 0409-1559-18 Single-dose vial
NDC 0409-1559-30 Carton of 10 | 75 mg/30 mL (2.5 mg/mL) | NDC 0409-1559-19 Single-dose vial
NDC 0409-1587-50 Carton of 1 | 125 mg/50 mL (2.5 mg/mL) | NDC 0409-1587-50 Multiple-dose vial
0.5% Contains 5 mg bupivacaine hydrochloride per mL.
NDC 0409-1560-10 Tray of 10 | 50 mg/10 mL (5 mg/mL) | NDC 0409-1560-18 Single-dose vial
NDC 0409-1560-29 Carton of 10 | 150 mg/30 mL (5 mg/mL) | NDC 0409-1560-19 Single-dose vial
NDC 0409-1610-50 Carton of 1 | 250 mg/50 mL (5 mg/mL) | NDC 0409-1610-50 Multiple-dose vial
0.75% Contains 7.5 mg bupivacaine hydrochloride per mL.
NDC 0409-1582-10 Tray of 10 | 75 mg/10 mL (7.5 mg/mL) | NDC 0409-1582-18 Single-dose vial
NDC 0409-1582-29 Carton of 10 | 225 mg/30 mL (7.5 mg/mL) | NDC 0409-1582-19 Single-dose vial

MARCAINE with epinephrine 1:200,000 (as bitartrate)―Solutions of MARCAINE that contain epinephrine should not be autoclaved and should be protected from light. Do not use the solution if its color is pinkish or darker than slightly yellow or if it contains a precipitate.

Unit of Sale | Concentration | Each
0 .25% with epinephrine 1:200,000 --- Contains 2.5 mg bupivacaine hydrochloride per mL.
NDC 0409-1746-10 Carton of 10 | 25 mg/10 mL (2.5 mg/mL) | NDC 0409-1746-70 Single-dose vial
NDC 0409-1746-30 Carton of 10 | 75 mg/30 mL (2.5 mg/mL) | NDC 0409-1746-71 Single-dose vial
NDC 0409-1752-50 Carton of 1 | 125 mg/50 mL (2.5 mg/mL) | NDC 0409-1752-50 Multiple-dose vial
0.5% with epinephrine 1:200,000 --- Contains 5 mg bupivacaine hydrochloride per mL.
NDC 0409-1749-10 Carton of 10 | 50 mg/10 mL (5 mg/mL) | NDC 0409-1749-70 Single-dose vial
NDC 0409-1749-29 Carton of 10 | 150 mg/30 mL (5 mg/mL) | NDC 0409-1749-71 Single-dose vial
NDC 0409-1755-50 Carton of 1 | 250 mg/50 mL (5 mg/mL) | NDC 0409-1755-50 Multiple-dose vial

For single-dose vials: Discard unused portion.

Distributed by Hospira, Inc.,

Lake Forest, IL 60045

USDA

Revised: 11/2018

PRINCIPAL DISPLAY PANEL: P-Care K40MX

NDC 49836-004-20

RX-Only

P-Care K40MX

Kit Contains:

1 KENALOG†-40 Single Dose Vial (1 mL)
1 MARCAINE† 0.5% Single Dose Vial (5 mg/mL) (10 mL)
1 XYLOCAINE† - MPF 1% Single Dose Vial (10 mg/mL) (5mL)
1 Sodium Chloride Injection, USP 0.9% Single Dose Vial (10mL)
1 Sterile Povidone-Iodine Swabsticks (3 Swabs)
1 Sterile Pair Nitrile Powder-Free Gloves (Size 7.5)
1 Sterile Towel Drape
1 Sterile Fenestrated Towel Drape
2 Sterile Adhesive Bandage
2 Sterile Adhesive Spot Bandage
3 Sterile Packs of 4x4 Gauze (6 Gauzes)
5 Sterile Isopropyl Alcohol 70% Prep Pad

Needles and Syringes Not Included

1 Dose

1 ONE NEEDLE,
ONE SYRINGE,
ONLY ONE TIME.
Safe Injection Practices Coalition
www.ONEandONLYcampaign.org

Members of One & Only Campaign

P-Care K40MX

DISTRIBUTED BY
SCHMIGS
HAUPPAUGE, NY 11788
NDC 49836-004-20

MANUFACTURED BY:
Rx Pharma Pack
HAUPPAUGE, NY 11788

Questions/Comments 1-844-632-7898

Kit Contents:

KENALOG†-40* (Bristol-Myers Squibb)
Triamcinolone Acetonide Injectable Suspension, USP

MARCAINE† 0.5% (5 mg/mL)* (Hospira, Inc)
Bupivacaine HCl Injection, USP

XYLOCAINE† - MPF 1% (10 mg/mL)* (APP Fresenius Kabi USA, LLC)
Lidocaine HCl Injection, USP

Sodium Chloride Injection, USP 0.9% (10 mL)* (APP Pharmaceuticals, LLC)

Sterile APLICARE† Povidone-Iodine Swabsticks* (Clorox Professional Products Company)

Sterile Nitrile Powder-Free Gloves* (Dynarex) - Size 7.5

Sterile Towel Drape* (Dynarex)

Sterile Fenestrated Towel Drape* (Dynarex)

Sterile Adhesive Bandage* (Dynarex)

Sterile Adhesive Spot Bandage* (Dynarex)

Sterile 4x4 Gauze* (Dynarex)

Sterile Alcohol Prep Pad 70% by Volume* (Dynarex)

† All trademarks and registered trademarks noted herein are the property of their respective owners.
* Internal package components remain sterile when stated as long as items are unopened and undamaged.

WARNING: KEEP THIS AND ALL MEDICATION
OUT OF THE REACH OF CHILDREN. IN CASE OF
ACCIDENTAL OVERDOSE, SEEK PROFESSIONAL
ASSISTANCE OR CONTACT A POISON CONTROL
CENTER IMMEDIATELY.

PROTECT FROM LIGHT I AVOID FREEZING

STORE AT CONTROLLED ROOM TEMPERATURE
20º-25ºC (68º-77º F) [SEE USP CONTROLLED
ROOM TEMPERATURE]

DO NOT REFRIGERATE.

For Single use Only.

Directions for Use: See enclosed inserts.

SUSTAINABLE Certified Sourcing
FORESTRY www.sfiprogram.org
INITIATIVE SFI-01376

ORG 04/2017

This product is not eligible for Medicare or Medicaid reimbursement.

P-Care K40MX